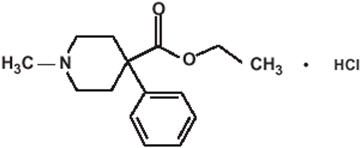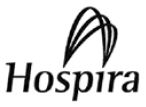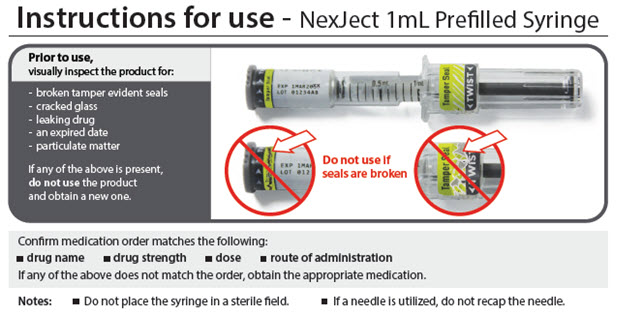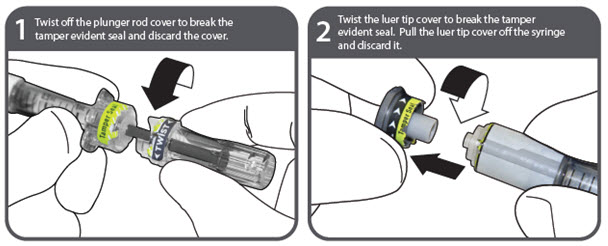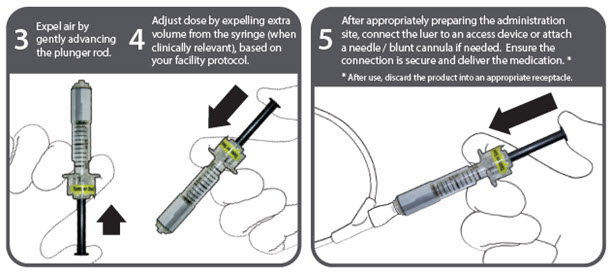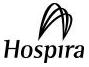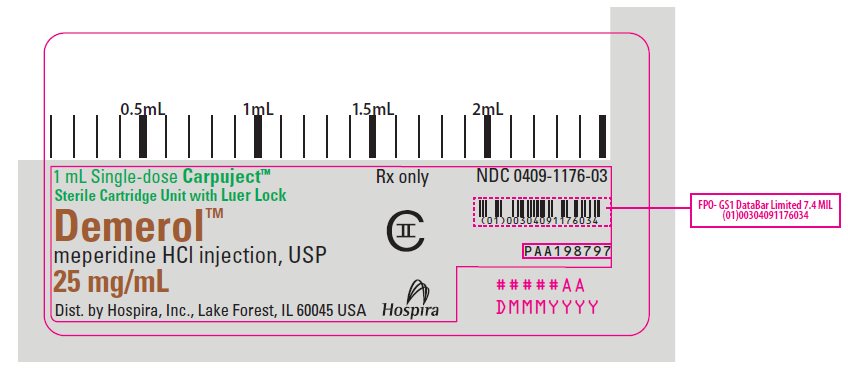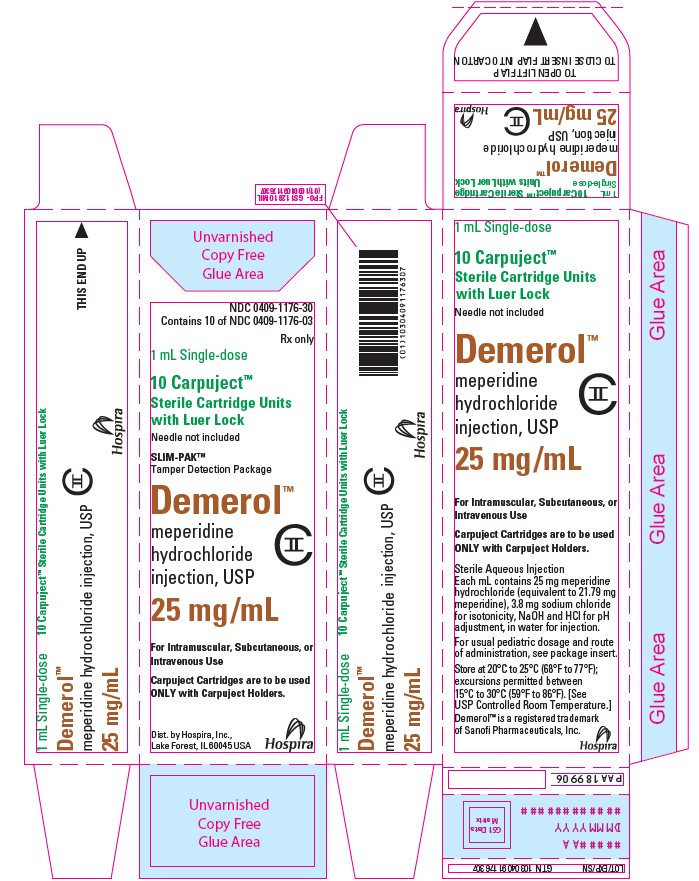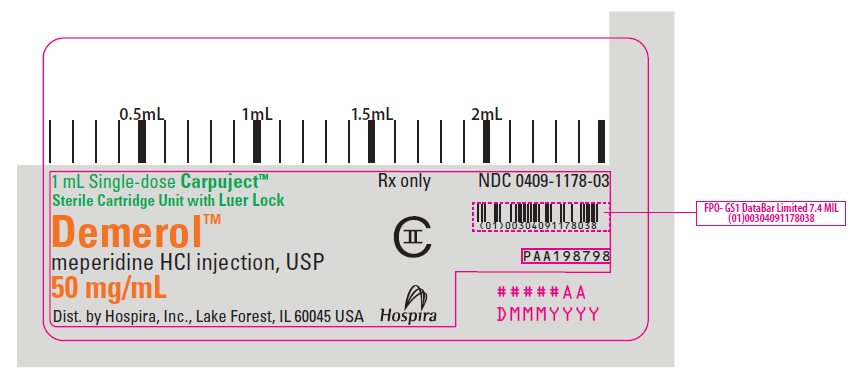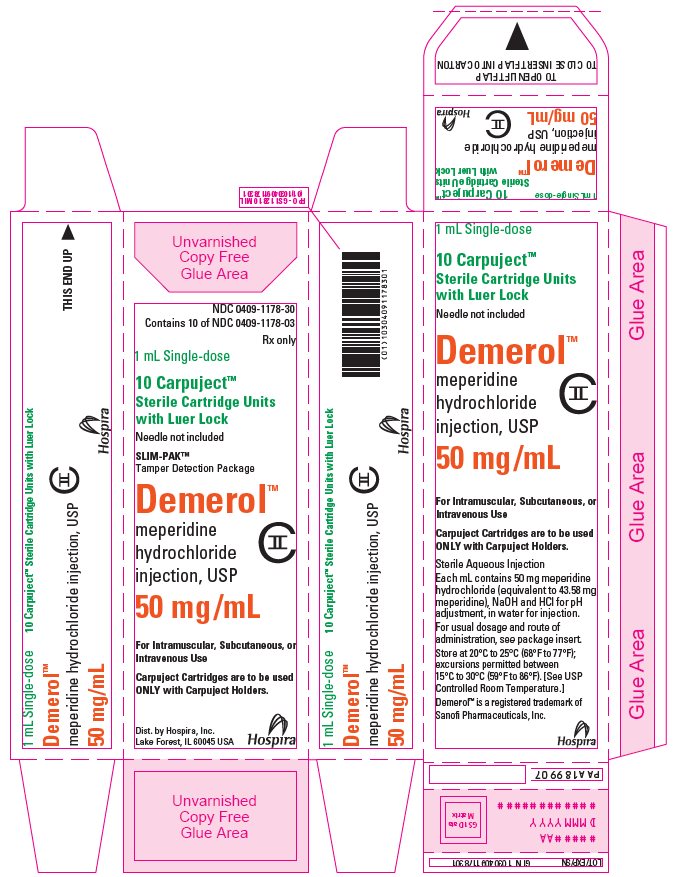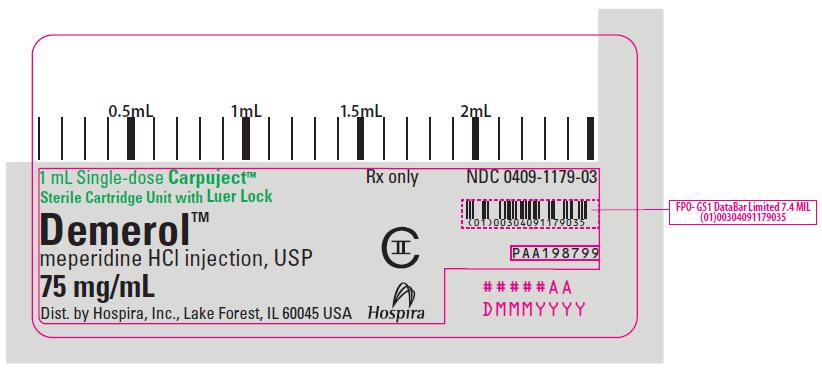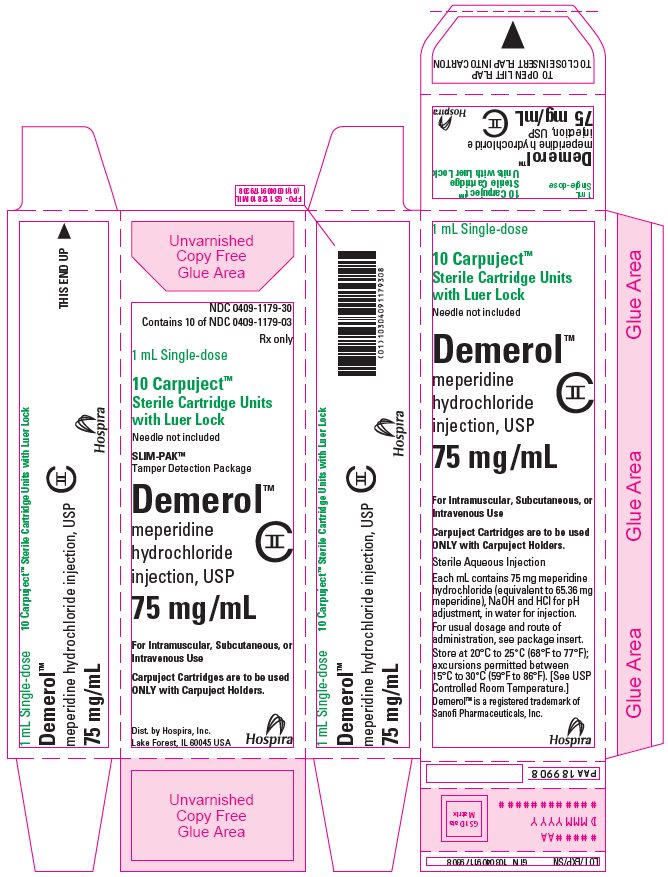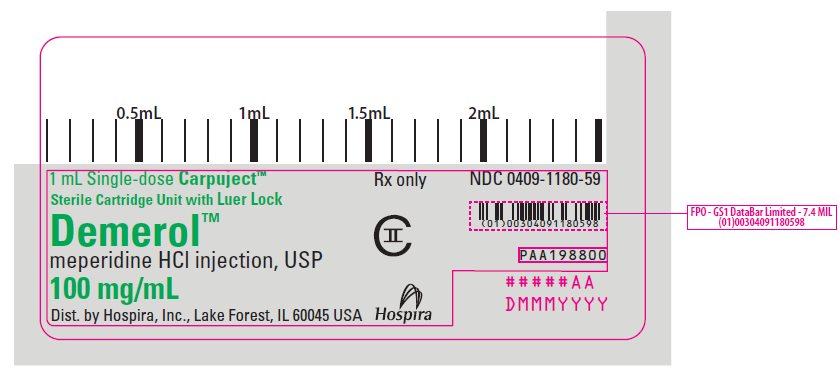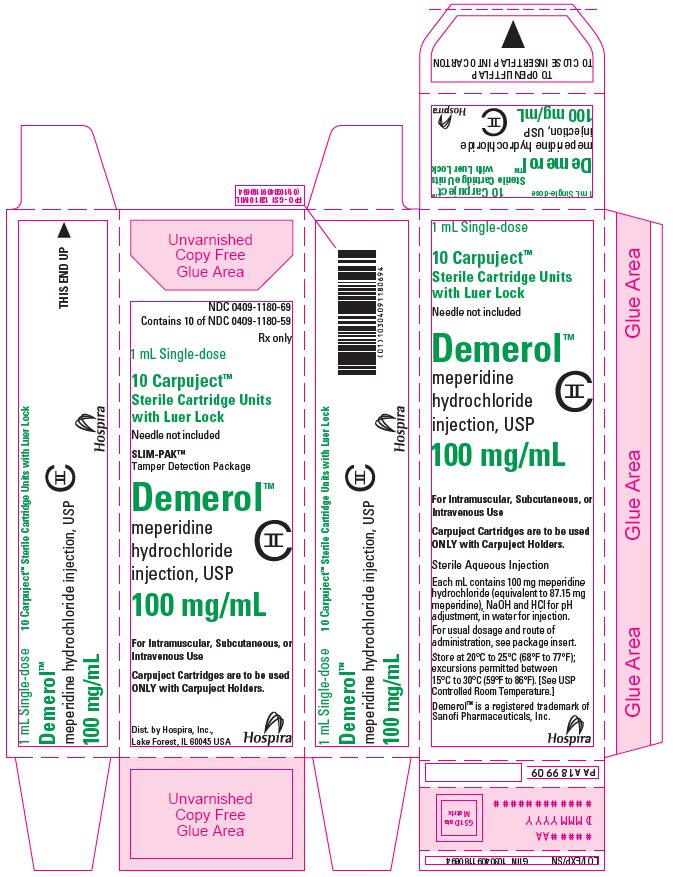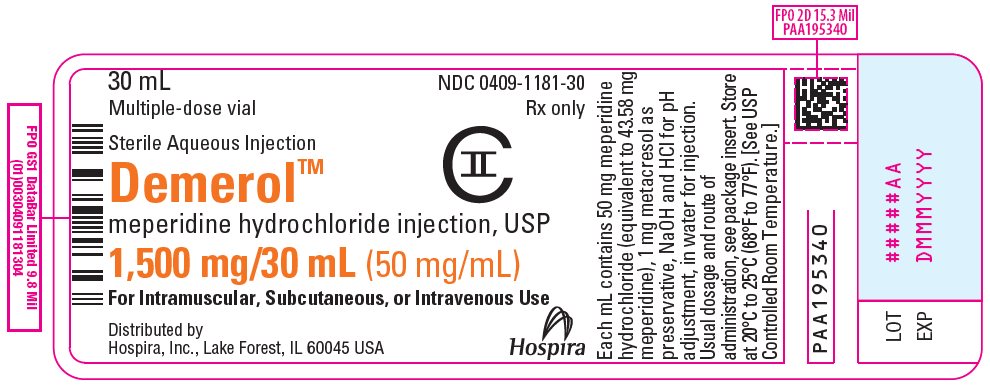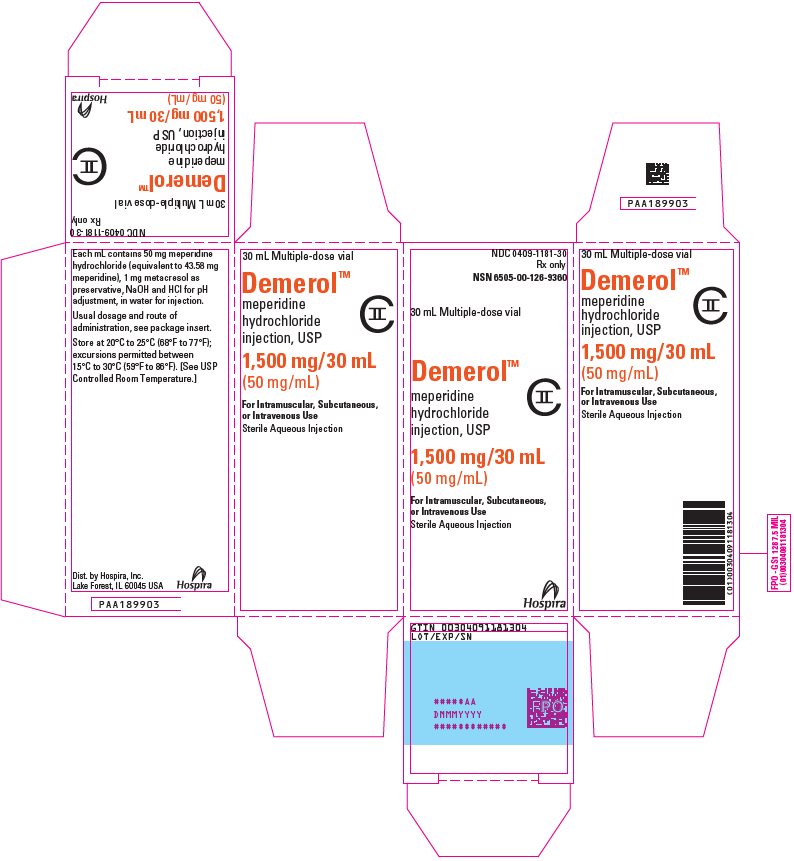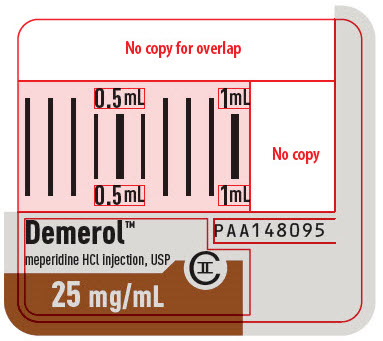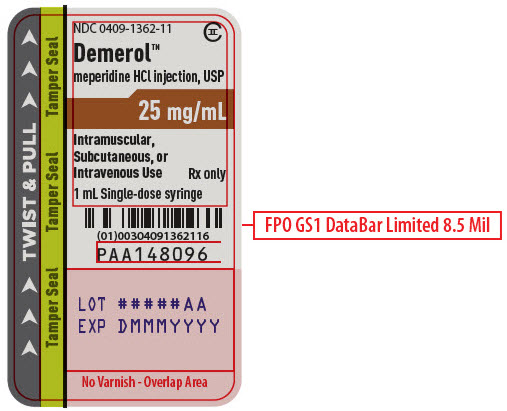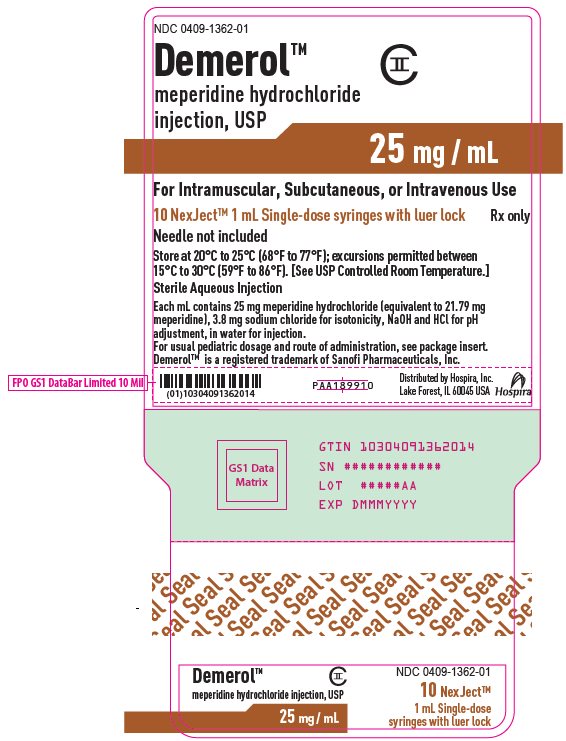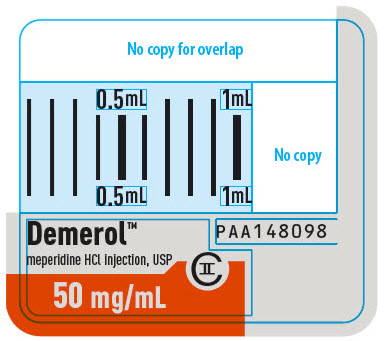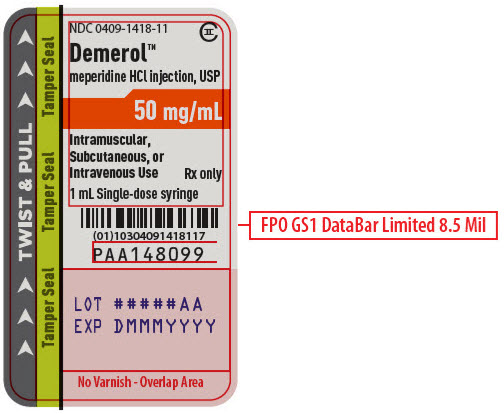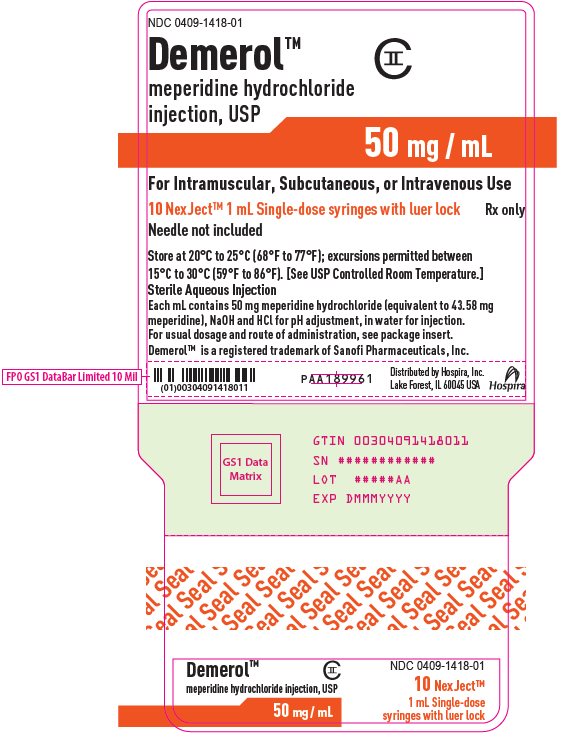 DRUG LABEL: DEMEROL
NDC: 0409-1181 | Form: INJECTION, SOLUTION
Manufacturer: Hospira, Inc.
Category: prescription | Type: HUMAN PRESCRIPTION DRUG LABEL
Date: 20251230
DEA Schedule: CII

ACTIVE INGREDIENTS: MEPERIDINE HYDROCHLORIDE 50 mg/1 mL
INACTIVE INGREDIENTS: SODIUM HYDROXIDE; HYDROCHLORIC ACID; METACRESOL; WATER

HIGHLIGHTS OF PRESCRIBING INFORMATION

These highlights do not include all the information needed to use DEMEROL™ INJECTION safely and effectively. See full prescribing information for DEMEROL INJECTION.
DEMEROL‎™ (meperidine hydrochloride injection), for subcutaneous, intramuscular, and intravenous use, CII
Initial U.S. Approval: 1942

RECENT MAJOR CHANGES

Boxed Warning | 12/2025
Indications and Usage (1) | 12/2025
Dosage and Administration (2.2)‎ | 12/2025
Warnings and Precautions (5.1, 5.2, 5.3, 5.13, 5.14, 5.15)‎ | 12/2025

WARNING: SERIOUS AND LIFE-THREATENING RISKS FROM USE OF DEMEROL ‎INJECTION

See full prescribing information for complete boxed warning.

- DEMEROL Injection exposes users to risks of addiction, abuse, and misuse, which can lead to overdose and death. Assess patient’s risk before prescribing and reassess regularly for these behaviors and conditions. (5.1)
- Serious, life-threatening, or fatal respiratory depression may occur with use of DEMEROL Injection, especially during initiation or following a dosage increase. To reduce the risk of respiratory depression, proper dosing and titration of ‎DEMEROL Injection are essential.‎ (5.2)
- Concomitant use of opioids with benzodiazepines or other central nervous system (CNS) depressants, including alcohol, may result in profound sedation, respiratory depression, coma, and death. Reserve concomitant prescribing for use in patients for whom alternative treatment options are inadequate. (5.3, 7)
- Advise pregnant women using opioids for an extended period of time of the risk of Neonatal Opioid Withdrawal Syndrome, which may be life-threatening if not ‎recognized and treated. Ensure that management by neonatology experts will be ‎available at delivery. (5.4)
- Concomitant use with CYP3A4 inhibitors (or discontinuation of CYP3A4 inducers) can result in a fatal overdose of meperidine. (5.5, 7)
- Concomitant use of DEMEROL Injection with Monoamine oxidase (MAO) inhibitors can result in coma, severe respiratory depression, cyanosis and hypotension. Use of DEMEROL Injection with MAO inhibitors is contraindicated. (4, 5.6, 7)

1 INDICATIONS AND USAGE

DEMEROL Injection is indicated for preoperative medication, support of anesthesia, for obstetrical analgesia, and for the management of pain severe enough to require an opioid analgesic and for which alternative treatments are inadequate. (1)

Limitations of Use

Because of the risks of addiction, abuse, misuse, overdose, and death, which can occur at any dosage or duration and persist over the course of therapy, reserve opioid analgesics, including DEMEROL Injection, for use in patients for whom alternative treatment options are ineffective, not tolerated, or would be otherwise inadequate to provide sufficient management of pain.

Use of ‎DEMEROL Injection for an extended period of time may increase the risk of ‎toxicity (e.g., seizures) from the accumulation of the meperidine metabolite, ‎normeperidine. (1, 5.1)‎

2 DOSAGE AND ADMINISTRATION

- DEMEROL Injection should be prescribed only by healthcare ‎professionals who are knowledgeable about the use of ‎opioids and how to mitigate the associated risks. (2.1)‎
- Use the lowest effective dosage for the shortest duration of time consistent with individual patient treatment goals. ‎Reserve titration to higher doses of DEMEROL ‎Injection for patients in whom lower doses are ‎insufficiently effective and in whom the expected benefits ‎of using a higher dose opioid clearly outweigh the ‎substantial risks. (2.1, 5)‎
- Many acute pain conditions (e.g., the pain that occurs with ‎a number of surgical procedures or acute ‎musculoskeletal injuries) require no more than a few ‎days of an opioid analgesic. Clinical guidelines on ‎opioid prescribing for some acute pain conditions are ‎available. (2.1)‎
- Initiate the dosing regimen for each patient individually, ‎taking into account the patient’s underlying cause and ‎severity of pain, prior analgesic treatment and ‎response, and risk factors for addiction, abuse, and ‎misuse. (2.1, 5.2)‎
- Respiratory depression can occur at any time during opioid ‎therapy, especially when initiating and following dosage ‎increases with DEMEROL Injection. Consider this risk ‎when selecting an initial dose and when making dose ‎adjustments. (2.2, 5.3)‎
- Periodically reassess patients receiving DEMEROL Injection to evaluate the continued need for opioid analgesics to maintain pain control, for the signs or symptoms of adverse reactions, and for the development of addiction, abuse, or misuse. (2.2)
- For Relief of Pain:
Titrate the dose based upon the individual patient’s response to their ‎initial dose of DEMEROL Injection. (2.2, 5)‎
  Adults: 50 mg to 150 mg intramuscularly or subcutaneously every 3 to 4 hours. (2.2)
  Children: 0.5 mg/lb to 0.8 mg/lb intramuscularly or subcutaneously up to the adult dose every 3 to 4 hours. (2.2)
- Preoperative Medication:
  Adults: 50 mg to 100 mg intramuscularly or subcutaneously, 30 to 90 minutes before beginning anesthesia. (2.3)
  Children: 0.5 mg/lb to 1 mg/lb intramuscularly or subcutaneously up to the adult dose, 30 to 90 minutes before beginning anesthesia. (2.3)
- Obstetrical Analgesia:
  50 mg to 100 mg intramuscularly or subcutaneously; may be repeated at 1 to 3 hour intervals. (2.4)
- Do not rapidly reduce or abruptly discontinue DEMEROL Injection in a physically‑dependent patient. (2.2, 5.15)

3 DOSAGE FORMS AND STRENGTHS

- Injectable, Carpuject™ Single-dose cartridge with Luer Lock for the Carpuject Syringe System, to be used ONLY with Carpuject™ Holder: 25 mg/mL, 50 mg/mL, 75 mg/mL, and 100 mg/mL. (3)
- Injectable, Multiple-dose vials: 1,500 mg/30 mL (50 mg/mL). (3)
- Injectable, NexJect™ Single-dose Prefilled Syringe with Luer Lock: 25 mg/mL and 50 mg/mL. (3)

4 CONTRAINDICATIONS

- Significant respiratory depression. (4)
- Acute or severe bronchial asthma in an unmonitored setting or in absence of resuscitative equipment. (4)
- Concurrent use of monoamine oxidase inhibitors (MAOIs) or use of MAOIs within the last 14 days. (7)
- Known or suspected gastrointestinal obstruction, including paralytic ileus. (4)
- Hypersensitivity to meperidine or to any other ingredients of the product. (4)

5 WARNINGS AND PRECAUTIONS

- Opioid-Induced Hyperalgesia and Allodynia: Opioid-Induced ‎Hyperalgesia (OIH) occurs when an opioid analgesic ‎paradoxically causes an increase in pain, or an increase in ‎sensitivity to pain. If OIH is suspected, carefully consider appropriately ‎decreasing the dose of the current opioid analgesic or ‎opioid rotation. (5.7)‎
- Serotonin Syndrome with Concomitant Use of Serotonergic Drugs: Potentially life-threatening condition could result from concomitant serotonergic drug administration. Discontinue DEMEROL Injection if serotonin syndrome is suspected. (5.8)
- Life-Threatening Respiratory Depression in Patients with Chronic Pulmonary Disease or in Elderly, Cachectic, or Debilitated Patients: Monitor closely, particularly during initiation and titration. (5.9)
- Adrenal Insufficiency: If diagnosed, treat with physiologic replacement of corticosteroids, and wean patient off of the opioid. (5.10)
- Severe Hypotension: Monitor during dosage initiation and titration. Avoid use of DEMEROL Injection in patients with circulatory shock. (5.11)
- Risks of Use in Patients with Increased Intracranial Pressure, Brain Tumors, Head Injury, or Impaired Consciousness: Monitor for sedation and respiratory depression. Avoid use of DEMEROL Injection in patients with impaired consciousness or coma. (5.12)

6 ADVERSE REACTIONS

Most common adverse reactions were lightheadedness, dizziness, sedation, nausea, vomiting and sweating. (6)

To report SUSPECTED ADVERSE REACTIONS, contact Pfizer, Inc. at 1-800-438-1985, or FDA at 1-800-FDA-1088 or www.fda.gov/medwatch.

7 DRUG INTERACTIONS

Mixed Agonist/Antagonist and Partial Agonist Opioid Analgesics: Avoid use with DEMEROL Injection because they may reduce analgesic effect of DEMEROL Injection or precipitate withdrawal symptoms. (7)

8 USE IN SPECIFIC POPULATIONS

- Pregnancy: May cause fetal harm. (8.1)
- Geriatric Patients: Use caution during dose selection, starting at the low ‎end of the dosing range while carefully monitoring for side effects. ‎‎(8.5)‎

FULL PRESCRIBING INFORMATION

WARNING: SERIOUS AND LIFE-THREATENING RISKS FROM USE OF DEMEROL

Addiction, Abuse, and Misuse

Because the use of DEMEROL Injection exposes patients and other users to the risks of opioid addiction, abuse, and misuse, which can lead to overdose and death, assess each patient’s risk prior to prescribing and reassess all patients regularly for the development of these behaviors and conditions [see Warnings and Precautions (5.1)].

Life-Threatening Respiratory Depression

Serious, life-threatening, or fatal respiratory depression may occur with use of DEMEROL Injection, especially during initiation or following a dosage increase. To reduce the risk of respiratory depression, ‎proper dosing and titration of DEMEROL Injection are essential [see Warnings and Precautions (5.2)].

Risks from Concomitant Use with Benzodiazepines or Other CNS Depressants

Concomitant use of opioids with benzodiazepines or other central nervous system (CNS) depressants, including alcohol, may result in profound sedation, respiratory depression, coma, and death. Reserve concomitant prescribing of DEMEROL Injection and benzodiazepines or other CNS depressants for use in patients for whom alternative treatment options are inadequate [see Warnings and Precautions (5.3), Drug Interactions (7)].

Neonatal Opioid Withdrawal Syndrome (NOWS)

Advise pregnant women using opioids for an extended period of time of the risk of Neonatal Opioid Withdrawal Syndrome, which may be life-threatening if not recognized and treated. Ensure that management by neonatology experts will be available at delivery [see Warnings and Precautions (5.4)].

Cytochrome P450 3A4 Interaction

The concomitant use of DEMEROL Injection with all cytochrome P450 3A4 inhibitors may result in an increase in meperidine plasma concentrations, which could increase or prolong adverse reactions and may cause potentially fatal respiratory depression. In addition, discontinuation of a concomitantly used cytochrome P450 3A4 inducer may result in an increase in meperidine plasma concentration. Monitor patients receiving DEMEROL Injection and any CYP3A4 inhibitor or inducer [see Warnings and Precautions (5.5), Drug Interactions (7)].

Concomitant Use of DEMEROL Injection with Monoamine Oxidase (MAO) Inhibitors

Concomitant use of DEMEROL Injection with monoamine oxidase (MAO) inhibitors can result in coma, severe respiratory depression, cyanosis, and hypotension. Use of DEMEROL Injection with MAO inhibitors within last 14 days is contraindicated [see Contraindications (4), Warnings and Precautions (5.6), Drug Interactions (7)].

1 INDICATIONS AND USAGE

DEMEROL Injection is indicated for preoperative medication, support of anesthesia, and obstetrical analgesia.

DEMEROL Injection is indicated for the management of pain severe enough to require an opioid analgesic and for which alternative treatments are inadequate.

Limitations of Use:

Because of the risks of addiction, abuse, misuse, overdose, and death, which can occur at any dosage or duration and persist over the course of therapy, [see Warnings and Precautions (5.1)], reserve opioid analgesics, including DEMEROL Injection, for use in patients for whom alternative treatment options are ineffective, not tolerated, or would be otherwise inadequate to provide sufficient management of pain.

Use of DEMEROL Injection for an extended period of time may increase the risk of toxicity (e.g., seizures) from the accumulation of the meperidine metabolite, normeperidine.

2 DOSAGE AND ADMINISTRATION

2.1 Important Dosage and Administration Instructions

- DEMEROL Injection should be prescribed only by healthcare professionals ‎who are knowledgeable about the use of opioids and how to mitigate the ‎associated risks.‎
- Use the lowest effective dosage for the shortest duration of time consistent with individual patient treatment goals [see Warnings and Precautions (5)]. Because the risk of overdose increases as opioid doses increase, reserve ‎titration to higher doses of DEMEROL Injection for patients in whom lower ‎doses are insufficiently effective and in whom the expected benefits of using a ‎higher dose opioid clearly outweigh the substantial risks.‎
- Many acute pain conditions (e.g., the pain that occurs with a number of surgical ‎procedures or acute musculoskeletal injuries) require no more than a few days of ‎an opioid analgesic. Clinical guidelines on opioid prescribing for some acute ‎pain conditions are available.‎
- There is variability in the opioid analgesic dose and duration needed to ‎adequately manage pain due both to the cause of pain and to individual patient ‎factors. ‎Initiate the dosing regimen for each patient individually, taking into account the patient's underlying cause and severity of pain, prior analgesic treatment and response, and risk factors for addiction, abuse, and misuse [see Warnings and Precautions (5.1)].
- Respiratory depression can occur at any time during opioid therapy, especially ‎when initiating and following dosage increases with DEMEROL Injection.‎ Consider this risk when selecting an initial dose and when making dose ‎adjustments [see Warnings and Precautions (5)].
- Inspect DEMEROL Injection for particulate matter and discoloration prior to administration. Do not use if color is darker than pale yellow, if it is discolored in any other way, or if it contains a ‎precipitate.‎

2.2 For Management of Pain

Initial Dosage

Dosage should be adjusted according to the severity of the pain and the response of the patient. While subcutaneous administration is suitable for occasional use, intramuscular administration is preferred when repeated doses are required. If intravenous administration is required, dosage should be decreased and the injection made very slowly, preferably utilizing a diluted solution.

Adults: Initiate treatment in a dosing range of 50 mg to 150 mg intramuscularly or subcutaneously every 3 to 4 hours as needed for pain, and at the lowest dose necessary to achieve adequate analgesia. Elderly patients should usually be given meperidine at the lower end of the dose range and observed closely.

Children: Initiate treatment in a dosing range of 0.5 mg/lb to 0.8 mg/lb intramuscularly or subcutaneously up to the adult dose, every 3 to 4 hours as necessary, and at the lowest dose necessary to achieve adequate analgesia.

Titration and Maintenance of Therapy

Titrate the dose based upon the individual patient’s response to their initial dose of DEMEROL Injection. Individually titrate DEMEROL Injection to a dose that provides adequate analgesia and minimizes adverse reactions. Continually reevaluate patients receiving DEMEROL Injection to assess the maintenance of pain control, signs and symptoms of opioid withdrawal, and other adverse reactions, as well as to reassess for the development of addiction, abuse, or misuse [see Warnings and Precautions (5.1, 5.15)]. Frequent communication is important among the prescriber, other members of the health and care team, the patient, and the caregiver/family during periods of changing analgesic requirements, including initial titration.

If the level of pain increases after dosage stabilization, attempt to identify the source of increased pain before increasing the DEMEROL Injection dosage. If after increasing the dosage, unacceptable opioid-related adverse reactions are observed (including an increase in pain after a dosage increase), consider reducing the dosage [see Warnings and Precautions ‎‎(5)]. Adjust the dosage to obtain an appropriate balance between management of pain and opioid-related adverse reactions.

Discontinuation of DEMEROL Injection

When a patient who has been taking DEMEROL Injection regularly and may be physically-dependent no longer requires therapy with DEMEROL Injection, taper the dose gradually, by 25% to 50% every 2 to 4 days, while monitoring carefully for signs and symptoms of withdrawal. If the patient develops these signs or symptoms, raise the dose to the previous level and taper more slowly, either by increasing the interval between decreases, decreasing the amount of change in dose, or both. Do not rapidly reduce or abruptly discontinue DEMEROL Injection in patients who may be physically dependent on opioids [see Warnings and Precautions (5.15), Drug Abuse and Dependence (9.3)].

2.3 For Preoperative Medication

Adults: The usual dosage is 50 mg to 100 mg intramuscularly or subcutaneously, 30 to 90 minutes before the beginning of anesthesia. Elderly patients should usually be given meperidine at the lower end of the dose range and observed closely.

Children: The usual dosage is 0.5 mg/lb to 1 mg/lb intramuscularly or subcutaneously up to the adult dose, 30 to 90 minutes before the beginning of anesthesia.

2.4 For Support of Anesthesia

Repeated slow intravenous Injections of fractional doses (e.g., 10 mg/mL) or continuous intravenous infusion of a more dilute solution (e.g., 1 mg/mL) should be used. The dose should be titrated to the needs of the patient and will depend on the premedication and type of anesthesia being employed, the characteristics of the particular patient, and the nature and duration of the operative procedure. Elderly patients should usually be given meperidine at the lower end of the dose range and observed closely.

2.5 For Obstetrical Analgesia

The usual dosage is 50 mg to 100 mg intramuscularly or subcutaneously when pain becomes regular, and may be repeated at 1- to 3-hour intervals.

2.6 Dosage Modifications with Concomitant Phenothiazines

The dose of DEMEROL Injection should be proportionately reduced (usually by 25 to 50 percent) when administered concomitantly with phenothiazines and many other tranquilizers since they potentiate the action of DEMEROL Injection.

3 DOSAGE FORMS AND STRENGTHS

DEMEROL Injection is a clear, colorless, sterile aqueous solution, available in the following dosage forms and strengths:

- Single-dose Carpuject‎™‎ cartridge with Luer Lock for the Carpuject Syringe System, ONLY to be used with Carpuject‎™‎ Holder, and available in the following strengths: 25 mg/mL, 50 mg/mL, 75 mg/mL, and 100 mg/mL.
- Multiple-dose vials containing 0.1% metacresol as a preservative, available in the following strength: 1,500 mg/30 mL (50 mg/mL).
- Single-dose NexJectTM Prefilled Syringe with Luer Lock, available in the following strengths: 25 mg/mL and 50 mg/mL.

4 CONTRAINDICATIONS

DEMEROL Injection is contraindicated in patients with:

- Significant respiratory depression [see Warnings and Precautions (5.2)]
- Acute or severe bronchial asthma in an unmonitored setting or in the absence of resuscitative equipment [see Warnings and Precautions (5.9)]
- Concurrent use of monoamine oxidase inhibitors (MAOIs) or use of MAOIs within the last 14 days [see Warnings and Precautions (5.6), Drug Interactions (7)]
- Known or suspected gastrointestinal obstruction, including paralytic ileus [see Warnings and Precautions (5.13)]
- Hypersensitivity to meperidine (e.g., anaphylaxis) [see Adverse Reactions (6)]

5 WARNINGS AND PRECAUTIONS

5.1 Addiction, Abuse, and Misuse

DEMEROL Injection contains meperidine, a Schedule II controlled substance. As an opioid, DEMEROL Injection exposes users to the risks of addiction, abuse, and misuse [see Drug Abuse and Dependence (9)].

Although the risk of addiction in any individual is unknown, it can occur in patients appropriately prescribed DEMEROL Injection. Addiction can occur at recommended dosages and if the drug is misused or abused. The risk of opioid-related overdose or overdose-related death is increased with higher opioid doses, and this risk persists over the course of therapy. In postmarketing studies, addiction, abuse, misuse, and fatal and non-fatal opioid overdose were observed in patients with long-term opioid use [see Adverse Reactions (6)].

Assess each patient's risk for opioid addiction, abuse, or misuse prior to prescribing DEMEROL Injection, and monitor all patients receiving DEMEROL Injection for the development of these behaviors and conditions. Risks are increased in patients with a personal or family history of substance abuse (including drug or alcohol abuse or addiction) or mental illness (e.g., major depression). The potential for these risks should not, however, prevent the proper management of pain in any given patient. Patients at increased risk may be prescribed opioids such as DEMEROL Injection but use in such patients necessitates intensive counseling about the risks and proper use of DEMEROL Injection along with intensive monitoring for signs of addiction, abuse, and misuse.

Opioids are sought for nonmedical use and are subject to diversion from ‎legitimate prescribed use. Strategies to reduce these risks include prescribing the drug in the smallest appropriate quantity. Contact local state professional licensing board or state-controlled substances authority for information on how to prevent and detect abuse or diversion of this product.

5.2 Life-Threatening Respiratory Depression

Serious, life-threatening, or fatal respiratory depression has been reported with the use of opioids, even when used as recommended. Respiratory depression, if not immediately recognized and treated, may lead to respiratory arrest and death. Management of respiratory depression may include close observation, supportive measures, and use of opioid overdose reversal agents (e.g., naloxone, nalmefene), depending on the patient's clinical status [see Overdosage (10)]. Carbon dioxide (CO2) retention from opioid-induced respiratory depression can exacerbate the sedating effects of opioids.

While serious, life-threatening, or fatal respiratory depression can occur at any time during the use of DEMEROL Injection, the risk is greatest during the initiation of therapy or following a dosage increase.

To reduce the risk of respiratory depression, proper dosing and titration of DEMEROL Injection are essential [see Dosage and Administration (2.3)]. Overestimating the DEMEROL Injection dosage when converting patients from another opioid product can result in a fatal overdose with the first dose.

Opioids can cause sleep-related breathing disorders including central sleep apnea (CSA) and sleep-related hypoxemia. Opioid use increases the risk of CSA in a dose-dependent fashion. In patients who present with CSA, consider decreasing the opioid dosage using best practices for opioid taper [see Dosage and Administration (2.2)].

5.3 Risks from Concomitant Use with Benzodiazepines or Other CNS Depressants

Profound sedation, respiratory depression, coma, and death may result from the concomitant use of DEMEROL Injection with benzodiazepines and/or other CNS depressants, including alcohol (e.g., non-benzodiazepine sedatives/hypnotics, anxiolytics, tranquilizers, muscle relaxants, general anesthetics, antipsychotics, gabapentinoids [gabapentin or pregabalin], and other opioids). Because of these risks, reserve concomitant prescribing of these drugs for use in patients for whom alternative treatment options are inadequate.

Observational studies have demonstrated that concomitant use of opioid analgesics and benzodiazepines increases the risk of drug-related mortality compared to use of opioid analgesics alone. Because of similar pharmacological properties, it is reasonable to expect similar risk with the concomitant use of other CNS depressant drugs with opioid analgesics [see Drug Interactions (7)].

If the decision is made to prescribe a benzodiazepine or other CNS depressant concomitantly with an opioid analgesic, prescribe the lowest effective dosages and minimum durations of concomitant use. In patients already receiving an opioid analgesic, prescribe a lower initial dose of the benzodiazepine or other CNS depressant than indicated in the absence of an opioid, and titrate based on clinical response. If an opioid analgesic is initiated in a patient already taking a benzodiazepine or other CNS depressant, prescribe a lower initial dose of the opioid analgesic, and titrate based on clinical response. Monitor patients closely for signs and symptoms of respiratory depression and sedation.

Advise both patients and caregivers about the risks of respiratory depression and sedation when DEMEROL Injection is used with benzodiazepines or other CNS depressants (including alcohol and illicit drugs). Advise patients not to drive or operate heavy machinery until the effects of concomitant use of the benzodiazepine or other CNS depressant have been determined. Screen patients for risk of substance use disorders, including opioid abuse and misuse, and warn them of the risk for overdose and death associated with the use of additional CNS depressants including alcohol and illicit drugs [see Drug Interactions (7)].

5.4 Neonatal Opioid Withdrawal Syndrome

Use of DEMEROL Injection for an extended period of time during pregnancy can result in withdrawal in the neonate. Neonatal opioid withdrawal syndrome, unlike opioid withdrawal syndrome in adults, may be life-threatening if not recognized and treated, and requires management according to protocols developed by neonatology experts. Observe newborns for signs of neonatal opioid withdrawal syndrome and manage accordingly. Advise pregnant women using opioids for an extended period of time of the risk of neonatal opioid withdrawal syndrome and ensure that management by neonatology experts will be available at delivery [see Use in Specific Populations (8.1)].

5.5 Risks of Concomitant Use or Discontinuation of Cytochrome P450 3A4 Inhibitors and Inducers

Concomitant use of DEMEROL Injection with a CYP3A4 inhibitor, such as macrolide antibiotics (e.g., erythromycin), azole-antifungal agents (e.g., ketoconazole), and protease inhibitors (e.g., ritonavir), may increase plasma concentrations of meperidine and prolong opioid adverse reactions, which may cause potentially fatal respiratory depression [see Warnings and Precautions (5.2)], particularly when an inhibitor is added after a stable dose of DEMEROL Injection is achieved. Similarly, discontinuation of a CYP3A4 inducer, such as rifampin, carbamazepine, and phenytoin, in DEMEROL Injection treated patients may increase meperidine plasma concentrations and prolong opioid adverse reactions. When using DEMEROL Injection with CYP3A4 inhibitors or discontinuing CYP3A4 inducers in DEMEROL Injection treated patients, monitor patients closely at frequent intervals and consider dosage reduction of DEMEROL Injection until stable drug effects are achieved [see Drug Interactions (7)].

Concomitant use of DEMEROL Injection with CYP3A4 inducers or discontinuation of a CYP3A4 inhibitor could decrease meperidine plasma concentrations, decrease opioid efficacy or, possibly, lead to a withdrawal syndrome in a patient who had developed physical dependence to meperidine. When using DEMEROL Injection with CYP3A4 inducers or discontinuing CYP3A4 inhibitors, monitor patients closely at frequent intervals and consider increasing the opioid dosage if needed to maintain adequate analgesia or if symptoms of opioid withdrawal occur [see Drug Interactions (7)].

5.6 Fatal Interaction with Monoamine Oxidase Inhibitors

Meperidine is contraindicated in patients who are receiving monoamine oxidase (MAO) inhibitors or those who have recently received such agents. Therapeutic doses of meperidine have occasionally precipitated unpredictable, severe, and occasionally fatal reactions in patients who have received such agents within 14 days. The mechanism of these reactions is unclear but may be related to a preexisting hyperphenylalaninemia. Some have been characterized by coma, severe respiratory depression, cyanosis, and hypotension, and have resembled the syndrome of acute opioid overdose. Serotonin syndrome with agitation, hyperthermia, diarrhea, tachycardia, sweating, tremors, and impaired consciousness may also occur. In other reactions the predominant manifestations have been hyperexcitability, convulsions, tachycardia, hyperpyrexia, and hypertension.

Do not use DEMEROL Injection in patients taking MAOIs or within 14 days of stopping such treatment. Intravenous hydrocortisone or prednisolone have been used to treat severe reactions, with the addition of intravenous chlorpromazine in those cases exhibiting hypertension and hyperpyrexia. The usefulness and safety of opioid overdose reversal agents in the treatment of these reactions is unknown.

5.7 Opioid-Induced Hyperalgesia and Allodynia

Opioid-Induced Hyperalgesia (OIH) occurs when an opioid analgesic ‎paradoxically causes an increase in pain, or an increase in sensitivity to pain. ‎This condition differs from tolerance, which is the need for increasing doses of opioids to maintain a defined effect [see Drug Abuse and Dependence (9.3)]. Symptoms of OIH ‎include (but may not be limited to) increased levels of pain upon opioid dosage ‎increase, decreased levels of pain upon opioid dosage decrease, or pain from ‎ordinarily non-painful stimuli (allodynia). These symptoms may suggest OIH only ‎if there is no evidence of underlying disease progression, opioid tolerance, ‎opioid withdrawal, or addictive behavior.‎

Cases of OIH have been reported, both with short-term and longer-term use of ‎opioid analgesics. Though the mechanism of OIH is not fully understood, ‎multiple biochemical pathways have been implicated. Medical literature suggests ‎a strong biologic plausibility between opioid analgesics and OIH and allodynia. If ‎a patient is suspected to be experiencing OIH, carefully consider appropriately ‎decreasing the dose of the current opioid analgesic or opioid rotation (safely ‎switching the patient to a different opioid moiety) [see Dosage and ‎Administration (2), Warnings and Precautions (5.15)].‎

5.8 Serotonin Syndrome with Concomitant Use of Serotonergic Drugs

Cases of serotonin syndrome, a potentially life-threatening condition, have been reported during concomitant use of meperidine with serotonergic drugs. Serotonergic drugs include selective serotonin reuptake inhibitors (SSRIs), serotonin and norepinephrine reuptake inhibitors (SNRIs), tricyclic antidepressants (TCAs), triptans, 5-HT3 receptor antagonists, drugs that affect the serotonergic neurotransmitter system (e.g., mirtazapine, trazodone, tramadol), certain muscle relaxants (i.e., cyclobenzaprine, metaxalone), and drugs that impair metabolism of serotonin (including MAO inhibitors, both those intended to treat psychiatric disorders and also others, such as linezolid and intravenous methylene blue) [see Drug Interactions (7)]. This may occur within the recommended dosage range.

Serotonin syndrome symptoms may include mental status changes (e.g., agitation, hallucinations, coma), autonomic instability (e.g., tachycardia, labile blood pressure, hyperthermia), neuromuscular aberrations (e.g., hyperreflexia, incoordination, rigidity), and/or gastrointestinal symptoms (e.g., nausea, vomiting, diarrhea) and can be fatal. The onset of symptoms generally occurs within several hours to a few days of concomitant use but may occur later than that. Discontinue DEMEROL Injection if serotonin syndrome is suspected.

5.9 Life-Threatening Respiratory Depression in Patients with Chronic Pulmonary Disease or in Elderly, Cachectic, or Debilitated Patients

The use of DEMEROL Injection in patients with acute or severe bronchial asthma in an unmonitored setting or in the absence of resuscitative equipment is contraindicated.

Patients with Chronic Pulmonary Disease: DEMEROL Injection treated patients with significant chronic obstructive pulmonary disease or cor pulmonale, and those with a substantially decreased respiratory reserve, hypoxia, hypercapnia, or preexisting respiratory depression are at increased risk of decreased respiratory drive including apnea, even at recommended dosages of DEMEROL Injection [see Warnings and Precautions (5.2)].

Elderly, Cachectic, or Debilitated Patients: Life-threatening respiratory depression is more likely to occur in elderly, cachectic, or debilitated patients because they may have altered pharmacokinetics or altered clearance compared to younger, healthier patients [see Warnings and Precautions (5.2)].

Monitor such patients closely, particularly when initiating and titrating DEMEROL Injection and when DEMEROL Injection is given concomitantly with other drugs that depress respiration [see Warnings and Precautions (5.2)].

Alternatively, consider the use of non-opioid analgesics in these patients.

5.10 Adrenal Insufficiency

Cases of adrenal insufficiency have been reported with opioid use, more often following greater than one month of use. Presentation of adrenal insufficiency may include non-specific symptoms and signs including nausea, vomiting, anorexia, fatigue, weakness, dizziness, and low blood pressure. If adrenal insufficiency is suspected, confirm the diagnosis with diagnostic testing as soon as possible. If adrenal insufficiency is diagnosed, treat with physiologic replacement doses of corticosteroids. Wean the patient off of the opioid to allow adrenal function to recover and continue corticosteroid treatment until adrenal function recovers. Other opioids may be tried as some cases reported use of a different opioid without recurrence of adrenal insufficiency. The information available does not identify any particular opioids as being more likely to be associated with adrenal insufficiency.

5.11 Severe Hypotension

DEMEROL Injection may cause severe hypotension including orthostatic hypotension and syncope in ambulatory patients. There is increased risk in patients whose ability to maintain blood pressure has already been compromised by a reduced blood volume or concurrent administration of certain CNS depressant drugs (e.g., phenothiazines or general anesthetics) [see Drug Interactions (7)]. Monitor these patients for signs of hypotension after initiating or titrating the dosage of DEMEROL Injection. In patients with circulatory shock, DEMEROL Injection may cause vasodilation that can further reduce cardiac output and blood pressure. Avoid the use of DEMEROL Injection in patients with circulatory shock.

5.12 Risks of Use in Patients with Increased Intracranial Pressure, Brain Tumors, Head Injury, or Impaired Consciousness

In patients who may be susceptible to the intracranial effects of CO2 retention (e.g., those with evidence of increased intracranial pressure or brain tumors), DEMEROL Injection may reduce respiratory drive, and the resultant CO2 retention can further increase intracranial pressure. Monitor such patients for worsening of signs of increasing intracranial pressure. Monitor such patients for signs of sedation and respiratory depression, particularly when initiating therapy with DEMEROL Injection.

Opioids may also obscure the clinical course in a patient with a head injury. Avoid the use of DEMEROL Injection in patients with impaired consciousness or coma.

5.13 Risks of Gastrointestinal Complications

DEMEROL Injection is contraindicated in patients with known or suspected gastrointestinal obstruction, including paralytic ileus.

The meperidine in DEMEROL Injection may cause spasm of the sphincter of Oddi. Opioids may cause increases in serum amylase. Monitor patients with biliary tract disease, including acute pancreatitis, for worsening symptoms.

Cases of opioid-induced esophageal dysfunction (OIED) have been reported in patients taking opioids. The risk of OIED may increase as the dose and/or duration of opioids increases. Regularly evaluate patients for signs and symptoms of OIED (e.g., dysphagia, regurgitation, non-cardiac chest pain), and if necessary, adjust opioid therapy as clinically appropriate [see Clinical Pharmacology (12.2)].

5.14 Seizures

Meperidine may increase the risk of having a seizure in patients with or without a pre-existing seizure disorder. Prolonged use of meperidine may also increase the risk of seizure due to the accumulation of the meperidine metabolite, normeperidine.

Monitor patients with a history of seizure disorder for worsening seizure control and advise patients and caregivers to get emergency medical help right away in the event of a known or suspected seizure.

5.15 Withdrawal

Avoid the use of mixed agonist/antagonist (e.g., pentazocine, nalbuphine, and butorphanol) or partial agonist (e.g., buprenorphine) analgesics in patients who are receiving a full opioid agonist analgesic, including DEMEROL Injection. In these patients, mixed agonist/antagonist and partial agonist analgesics may reduce the analgesic effect and/or precipitate withdrawal symptoms.

When discontinuing DEMEROL Injection, gradually taper the dosage [see Dosage and Administration (2.2)]. Do not rapidly reduce or abruptly discontinue DEMEROL Injection [see Drug Abuse and Dependence (9.3)].

5.16 Risks of Driving and Operating Machinery

DEMEROL Injection may impair the mental or physical abilities needed to perform potentially hazardous activities such as driving a car or operating machinery. Warn patients not to drive or operate dangerous machinery unless they are tolerant to the effects of DEMEROL Injection and know how they will react to the medication.

5.17 Risks in Patients with Pheochromocytoma

In patients with pheochromocytoma, meperidine has been reported to provoke hypertension.

5.18 Risk of Use in Patients with Atrial Flutter and Other Supraventricular Tachycardias

DEMEROL Injection should be used with caution in patients with atrial flutter and other supraventricular tachycardias because of a possible vagolytic action which may produce a significant increase in the ventricular response rate.

5.19 Intravenous Use

If necessary, meperidine may be given intravenously, but the injection should be given very slowly, preferably in the form of a diluted solution. Rapid intravenous injection of opioid analgesics, including meperidine, increases the incidence of adverse reactions; severe respiratory depression, apnea, hypotension, peripheral circulatory collapse, and cardiac arrest have occurred. Meperidine should not be administered intravenously unless an opioid overdose reversal agent and the facilities for assisted or controlled respiration are immediately available. When meperidine is given parenterally, especially intravenously, the patient should be lying down.

6 ADVERSE REACTIONS

The following serious adverse reactions are described, or described in greater detail, in other sections:

- Addiction, Abuse, and Misuse [see Warnings and Precautions (5.1)]
- Life-Threatening Respiratory Depression [see Warnings and Precautions (5.2)]
- Interactions with Benzodiazepines or Other CNS Depressants [see Warnings and Precautions (5.3)]
- Neonatal Opioid Withdrawal Syndrome [see Warnings and Precautions (5.4)]
- Opioid-Induced Hyperalgesia and Allodynia [see Warnings and Precautions (5.7)]‎
- Serotonin Syndrome with Concomitant Use of Serotonergic Drugs [see Warnings and Precautions (5.8)]
- Adrenal Insufficiency [see Warnings and Precautions (5.10)]
- Severe Hypotension [see Warnings and Precautions (5.11)]
- Gastrointestinal Adverse Reactions [see Warnings and Precautions (5.13)]
- Seizures [see Warnings and Precautions (5.14)]
- Withdrawal [see Warnings and Precautions (5.15)]

The following adverse reactions associated with the use of meperidine were identified in clinical studies or postmarketing reports. Because some of these reactions were reported voluntarily from a population of uncertain size, it is not always possible to reliably estimate their frequency or establish a causal relationship to drug exposure.

The major hazards of meperidine, as with other opioid analgesics, are respiratory depression and, to a lesser degree, circulatory depression; respiratory arrest, shock, and cardiac arrest have occurred.

The most frequently observed adverse reactions include lightheadedness, dizziness, sedation, nausea, vomiting, and sweating. These effects seem to be more prominent in ambulatory patients and in those who are not experiencing severe pain. In such individuals, lower doses are advisable. Some adverse reactions in ambulatory patients may be alleviated if the patient lies down.

Other adverse reactions include:

Nervous System: Mood changes (e.g., euphoria, dysphoria), weakness, headache, agitation, tremor, involuntary muscle movements (e.g., muscle twitches, myoclonus), severe convulsions, seizures, transient hallucinations and disorientation, confusion, delirium, visual disturbances.

Inadvertent injection about a nerve trunk may result in sensory-motor paralysis which is usually, though not always, transitory.

Gastrointestinal: Dry mouth, constipation, biliary tract spasm.
Cardiovascular: Flushing of the face, tachycardia, bradycardia, palpitation, hypotension [see Warnings and Precautions (5.18)], syncope, phlebitis following intravenous injection.
Genitourinary: Urinary retention.
Allergic: Pruritus, urticaria, other skin rashes, wheal and flare over the vein with intravenous injection.
Hypersensitivity reactions, anaphylaxis.
Histamine release leading to hypotension and/or tachycardia, flushing, sweating, and pruritus.
Other: Pain at injection site; local tissue irritation and induration following subcutaneous injection, particularly when repeated; antidiuretic effect.
Serotonin syndrome: Cases of serotonin syndrome, a potentially life-threatening condition, have been reported during concomitant use of opioids with serotonergic drugs.
Adrenal insufficiency: Cases of adrenal insufficiency have been reported with opioid use, more often following greater than one month of use.
Androgen deficiency: Cases of androgen deficiency have occurred with use of opioids for an extended period of time [see Clinical Pharmacology (12.2)].
Hyperalgesia and Allodynia: Cases of hyperalgesia and allodynia have been ‎reported with opioid therapy of any duration [see Warnings and Precautions ‎‎(5.7)]‎.
Hypoglycemia: Cases of hypoglycemia have been reported in patients ‎taking opioids. Most reports were in patients with at least one ‎predisposing risk factor (e.g., diabetes).‎

Opioid-induced esophageal dysfunction (OIED): Cases of OIED have been reported in patients taking opioids and may occur more frequently in patients taking higher doses of opioids, and/or in patients taking opioids longer term [see Warnings and Precautions (5.13)].

Adverse Reactions from Observational Studies

A prospective, observational cohort study estimated the risks of addiction, abuse, and misuse in patients initiating long-term use of Schedule II opioid analgesics between 2017 and 2021. Study participants included in one or more analyses had been enrolled in selected insurance plans or health systems for at least one year, were free of at least one outcome at baseline, completed a minimum number of follow-up assessments, and either: 1) filled multiple extended-release/long-acting opioid analgesic prescriptions during a 90‑day period (n=978); or 2) filled any Schedule II opioid analgesic prescriptions covering at least 70 of 90 days (n=1,244). Those included also had no dispensing of the qualifying opioids in the previous 6 months.

Over 12 months:

- approximately 1% to 6% of participants across the two cohorts newly met criteria for addiction, as assessed with two validated interview-based measures of moderate-to-severe opioid use disorder based on Diagnostic and Statistical Manual of Mental Disorders, Fifth Edition (DSM-5) criteria, and
- approximately 9% and 22% of participants across the two cohorts newly met criteria for prescription opioid abuse and misuse [defined in Drug Abuse and Dependence (9.2)], respectively, as measured with a validated self-reported instrument.

A retrospective, observational cohort study estimated the risk of opioid-involved overdose or opioid overdose-related death in patients with new long-term use of Schedule II opioid analgesics from 2006 through 2016 (n=220,249). Included patients had been enrolled in either one of two commercial insurance programs, one managed care program, or one Medicaid program for at least 9 months. New long-term use was defined as having Schedule II opioid analgesic prescriptions covering at least 70 days’ supply over the 3 months prior to study entry and none during the preceding 6 months. Patients were excluded if they had an opioid-involved overdose in the 9 months prior to study entry. Overdose was measured using a validated medical code-based algorithm with linkage to the National Death Index database. The 5-year cumulative incidence estimates for opioid-involved overdose or opioid overdose-related death ranged from approximately 1.5% to 4% across study sites, counting only the first event during follow-up. Approximately 17% of first opioid overdoses observed over the entire study period (5-11 years, depending on the study site) were fatal. Higher baseline opioid dose was the strongest and most consistent predictor of opioid-involved overdose or opioid overdose-related death. Study exclusion criteria may have selected patients at lower risk of overdose, and substantial loss to follow-up (approximately 80%) also may have biased estimates.

The risk estimates from the studies described above may not be generalizable to all patients receiving opioid analgesics, such as those with exposures shorter or longer than the duration evaluated in the studies.

7 DRUG INTERACTIONS

Table 1 includes clinically significant drug interactions with DEMEROL Injection.

Table 1: Clinically Significant Drug Interactions with DEMEROL Injection
Monoamine Oxidase Inhibitors (MAOIs)
Clinical Impact: | Meperidine is contraindicated in patients who are receiving monoamine oxidase (MAO) inhibitors or those who have recently received such agents. Therapeutic doses of meperidine have occasionally precipitated unpredictable, severe, and occasionally fatal reactions in patients who have received such agents within 14 days. The mechanism of these reactions is unclear but may be related to a preexisting hyperphenylalaninemia. Some have been characterized by coma, severe respiratory depression, cyanosis, and hypotension, and have resembled the syndrome of acute opioid overdose. Serotonin syndrome with agitation, hyperthermia, diarrhea, tachycardia, sweating, tremors, and impaired consciousness may also occur. In other reactions the predominant manifestations have been hyperexcitability, convulsions, tachycardia, hyperpyrexia, and hypertension [see Warnings and Precautions (5.6)]‎.
Intervention: | Do not use DEMEROL Injection in patients taking MAOIs or within 14 days of stopping such treatment.; Intravenous hydrocortisone or prednisolone have been used to treat severe reactions, with the addition of intravenous chlorpromazine in those cases exhibiting hypertension and hyperpyrexia. The usefulness and safety of opioid overdose reversal agents in the treatment of these reactions are unknown.
Examples: | Phenelzine, tranylcypromine, linezolid
Inhibitors of CYP3A4 and CYP2B6
Clinical Impact: | The concomitant use of DEMEROL Injection and CYP3A4 or CYP2B6 inhibitors can increase the plasma concentration of meperidine, resulting in increased or prolonged opioid effects. These effects could be more pronounced with concomitant use of DEMEROL Injection and CYP2B6 and CYP3A4 inhibitors, particularly when an inhibitor is added after a stable dose of DEMEROL Injection is achieved [see Warnings and Precautions (5.5)].; After stopping a CYP3A4 inhibitor, as the effects of the inhibitor decline, the meperidine plasma concentration will decrease [see Clinical Pharmacology (12.3)], potentially resulting in decreased opioid efficacy or a withdrawal syndrome in patients who had developed physical dependence to meperidine.
Intervention: | If concomitant use is necessary, consider dosage reduction of DEMEROL Injection until stable drug effects are achieved. Monitor patients for respiratory depression and sedation at frequent intervals.; If a CYP3A4 or CYP2B6 inhibitor is discontinued, consider increasing the DEMEROL Injection dosage until stable drug effects are achieved.; Monitor for signs of opioid withdrawal.
Examples: | Macrolide antibiotics (e.g., erythromycin), azole-antifungal agents (e.g., ketoconizole), protease inhibitors (e.g., ritonavir)
CYP3A4 and CYP2B6 Inducers
Clinical Impact: | The concomitant use of DEMEROL Injection and CYP3A4 inducers or CYP2B6 inducers can decrease the plasma concentration of meperidine [see Clinical Pharmacology (12.3)], resulting in decreased efficacy or onset of a withdrawal syndrome in patients who have developed physical dependence to meperidine [see Warnings and Precautions (5.5)].; After stopping a CYP3A4 or CYP2B6 inducer, as the effects of the inducer decline, the meperidine plasma concentration will increase [see Clinical Pharmacology (12.3)], which could increase or prolong both the therapeutic effects and adverse reactions and may cause serious respiratory depression.
Intervention: | If concomitant use is necessary, consider increasing the DEMEROL Injection dosage until stable drug effects are achieved. Monitor for signs of opioid withdrawal. If a CYP3A4 or CYP2B6 inducer is discontinued, consider DEMEROL Injection dosage reduction and monitor for signs of respiratory depression.
Examples: | Rifampin, carbamazepine, phenytoin
Benzodiazepines and Other Central Nervous System (CNS) Depressants
Clinical Impact: | Due to additive pharmacologic effect, the concomitant use of benzodiazepines or other CNS depressants, including alcohol, can increase the risk of hypotension respiratory depression, profound sedation, coma, and death [see Warnings and Precautions (5.3)].
Intervention: | Reserve concomitant prescribing of these drugs for use in patients for whom alternative treatment options are inadequate. Limit dosages and durations to the minimum required. Monitor patients closely for signs of respiratory depression and sedation.
Examples: | Benzodiazepines and other sedatives/hypnotics, anxiolytics, tranquilizers, muscle relaxants, general anesthetics, antipsychotics, gabapentinoids (gabapentin or pregabalin), other opioids, alcohol.
Serotonergic Drugs
Clinical Impact: | The concomitant use of opioids with other drugs that affect the serotonergic neurotransmitter system has resulted in serotonin syndrome [see Warnings and Precautions (5.8)].
Intervention: | If concomitant use is warranted, carefully observe the patient, particularly during treatment initiation and dose adjustment. Discontinue DEMEROL Injection if serotonin syndrome is suspected.
Examples: | Selective serotonin reuptake inhibitors (SSRIs), serotonin and norepinephrine reuptake inhibitors (SNRIs), tricyclic antidepressants (TCAs), triptans, 5-HT3 receptor antagonists, drugs that affect the serotonin neurotransmitter system (e.g., mirtazapine, trazodone, tramadol), certain muscle relaxants (i.e., cyclobenzaprine, metaxalone), monoamine oxidase (MAO) inhibitors (those intended to treat psychiatric disorders and also others, such as linezolid and intravenous methylene blue).
Mixed Agonist/Antagonist and Partial Agonist Opioid Analgesics
Clinical Impact: | May reduce the analgesic effect of DEMEROL Injection and/or precipitate withdrawal symptoms.
Intervention: | Avoid concomitant use.
Examples: | Butorphanol, nalbuphine, pentazocine, buprenorphine.
Muscle Relaxants
Clinical Impact: | Meperidine may enhance the neuromuscular blocking action of skeletal muscle relaxants and produce an increased degree of respiratory depression.
Intervention: | Monitor patients for signs of respiratory depression that may be greater than otherwise expected and decrease the dosage of DEMEROL Injection and/or the muscle relaxant as necessary.
Examples: | Cyclobenzaprine, metaxalone
Diuretics
Clinical Impact: | Opioids can reduce the efficacy of diuretics by inducing the release of antidiuretic hormone.
Intervention: | Monitor patients for signs of diminished diuresis and/or effects on blood pressure and increase the dosage of the diuretic as needed.
Anticholinergic Drugs
Clinical Impact: | The concomitant use of anticholinergic drugs may increase risk of urinary retention and/or severe constipation, which may lead to paralytic ileus.
Intervention: | Monitor patients for signs of urinary retention or reduced gastric motility when DEMEROL Injection is used concomitantly with anticholinergic drugs.
Acyclovir
Clinical Impact: | The concomitant use of acyclovir may increase the plasma concentrations of meperidine and its metabolite, normeperidine.
Intervention: | If concomitant use of acyclovir and DEMEROL Injection is necessary, monitor patients for respiratory depression and sedation at frequent intervals.
Cimetidine
Clinical Impact: | The concomitant use of cimetidine may reduce the clearance and volume of distribution of meperidine also the formation of the metabolite, normeperidine, in healthy subjects
Intervention: | If concomitant use cimetidine and DEMEROL Injection is necessary, monitor patients for respiratory depression and sedation at frequent intervals.

8 USE IN SPECIFIC POPULATIONS

8.1 Pregnancy

Risk Summary

Use of opioid analgesics for an extended period of time during pregnancy may cause neonatal opioid withdrawal syndrome [see Warnings and Precautions (5.4)]. Available data with DEMEROL Injection are insufficient to inform a drug-associated risk for major birth defects and miscarriage or adverse maternal outcomes. There are adverse outcomes reported with fetal exposure to opioid analgesics [see Clinical Considerations]. Formal animal reproduction studies have not been conducted with meperidine. Neural tube defects (exencephaly and cranioschisis) have been reported in hamsters administered a single bolus dose of meperidine during a critical period of organogenesis at 0.85 and 1.5 times the total human daily dose of 1200 mg [see Data].

The background risk of major birth defects and miscarriage for the indicated population is unknown. All ‎‎pregnancies have a background risk of birth defect, loss, or other adverse outcomes. In the U.S. general population, the estimated background risk of major birth defects and miscarriage in clinically recognized pregnancies is 2 to 4% and 15 to 20%, respectively.

Clinical Considerations

Fetal/Neonatal Adverse Reactions

Use of opioid analgesics for an extended period of time during pregnancy for medical or nonmedical purposes can result in physical dependence in the neonate and neonatal opioid withdrawal syndrome shortly after birth.

Neonatal opioid withdrawal syndrome presents as irritability, hyperactivity and abnormal sleep pattern, high pitched cry, tremor, vomiting, diarrhea, and failure to gain weight. The onset, duration, and severity of neonatal opioid withdrawal syndrome vary based on the specific opioid used, duration of use, timing and amount of last maternal use, and rate of elimination of the drug by the newborn. Observe newborns for symptoms of neonatal opioid withdrawal syndrome and manage accordingly [see Warnings and Precautions (5.4)].

Labor or Delivery

Opioids cross the placenta and may produce respiratory depression and psycho-physiologic effects in neonates. An opioid overdose reversal agents, such as naloxone or nalmefene, must be available for reversal of opioid-induced respiratory depression in the neonate. DEMEROL Injection is not recommended for use in pregnant women during or immediately prior to labor, when other analgesic techniques are more appropriate. Opioid analgesics, including DEMEROL Injection, can prolong labor through actions which temporarily reduce the strength, duration, and frequency of uterine contractions. However, this effect is not consistent and may be offset by an increased rate of cervical dilation, which tends to shorten labor. Monitor neonates exposed to opioid analgesics during labor for signs of excess sedation and respiratory depression.

Data

Animal Data

Formal reproductive and developmental toxicology studies for meperidine have not been completed.

In a published study, neural tube defects (exencephaly and cranioschisis) were noted following subcutaneous administration of meperidine hydrochloride (127 and 218 mg/kg, respectively) on Gestation Day 8 to pregnant hamsters (0.85 and 1.5 times the total daily dose of 1200 mg/day based on body surface area). The findings cannot be clearly attributed to maternal toxicity.

8.2 Lactation

Risk Summary

Meperidine appears in the milk of nursing mothers receiving the drug. The developmental and health benefits of breastfeeding should be considered along with the mother's clinical need for DEMEROL Injection and any potential adverse effects on the breastfed infant from DEMEROL Injection or from the underlying maternal condition.

Clinical Considerations

Monitor infants exposed to DEMEROL Injection through breast milk for excess sedation and respiratory depression. Withdrawal symptoms can occur in breastfed infants when maternal administration of an opioid analgesic is stopped, or when breastfeeding is stopped.

8.3 Females and Males of Reproductive Potential

Infertility

Use of opioids for an extended period of time may cause reduced fertility in females and males of reproductive potential. It is not known whether these effects on fertility are reversible [see Adverse Reactions (6), Clinical Pharmacology (12.2), Nonclinical Pharmacology (13.1)].

8.4 Pediatric Use

The safety and efficacy of DEMEROL Injection in patients less than 18 years of age have not been established.

The safety and effectiveness of meperidine in pediatric patients has not been established. Literature reports indicate that meperidine has a slower elimination rate in neonates and young infants compared to older children and adults. Neonates and young infants may also be more susceptible to the effects, especially the respiratory depressant effects. If meperidine use is contemplated in neonates or young infants, any potential benefits of the drug need to be weighed against the relative risk of the patient.

8.5 Geriatric Use

Elderly patients (aged 65 years or older) may have increased sensitivity to meperidine. In general, use caution when selecting a dosage for an elderly patient, usually starting at the low end of the dosing range, reflecting the greater frequency of decreased hepatic, renal, or cardiac function and of concomitant disease or other drug therapy.

Respiratory depression is the chief risk for elderly patients treated with opioids, and has occurred after large initial doses were administered to patients who were not opioid-tolerant or when opioids were co-administered with other agents that depress respiration. Titrate the dosage of DEMEROL Injection slowly in geriatric patients and monitor closely for signs of central nervous system and respiratory depression [see Warnings and Precautions (5.2)].

Meperidine is known to be substantially excreted by the kidney, and the risk of adverse reactions to this drug may be greater in patients with impaired renal function. Because elderly patients are more likely to have decreased renal function, care should be taken in dose selection, and it may be useful to monitor renal function.

8.6 Hepatic Impairment

Accumulation of meperidine and/or its active metabolite, normeperidine, can also occur in patients with hepatic impairment. Elevated serum levels have been reported to cause central nervous system excitatory effects. Meperidine should therefore be used with caution in patients with hepatic impairment. Titrate the dosage of DEMEROL Injection slowly in patients with hepatic impairment and monitor closely for signs of central nervous system and respiratory depression.

8.7 Renal Impairment

Accumulation of meperidine and/or its active metabolite, normeperidine, can occur in patients with renal impairment. Meperidine should therefore be used with caution in patients with renal impairment. Titrate the dosage of DEMEROL Injection slowly in patients with renal impairment and monitor closely for signs of central nervous system and respiratory depression.

9 DRUG ABUSE AND DEPENDENCE

9.1 Controlled Substance

DEMEROL Injection contains meperidine, a Schedule II controlled substance.

9.2 Abuse

DEMEROL Injection contains meperidine, a substance with high potential for misuse and abuse, which can lead to the development of substance use disorder, including addiction [see Warnings and Precautions (5.1)].

Misuse is the intentional use, for therapeutic purposes, of a drug by an ‎individual in a way other than prescribed by a healthcare provider or for ‎whom it was not prescribed.‎

Abuse is the intentional, non-therapeutic use of a drug, even once, for its desirable psychological or physiological effects.

Drug addiction is a cluster of behavioral, cognitive, and physiological phenomena that may include a strong desire to take the drug, difficulties in controlling ‎drug use (e.g., continuing drug use despite harmful consequences, giving ‎a higher priority to drug use than other activities and obligations), and ‎possible tolerance or physical dependence.‎

Misuse and abuse of DEMEROL Injection increases risk of overdose, ‎which may lead to central nervous system and respiratory depression, ‎hypotension, seizures, and death. The risk is increased with concurrent ‎abuse of DEMEROL Injection with alcohol and/or other CNS depressants. Abuse of and addiction to opioids in some ‎individuals may not be accompanied by concurrent tolerance and ‎symptoms of physical dependence. In addition, abuse of opioids can occur ‎in the absence of addiction.‎

All patients treated with opioids require careful and frequent reevaluation for signs of misuse, abuse and addiction, because use of opioid analgesic products carries the risk of addiction even under appropriate medical use. ‎Patients at high risk of DEMEROL Injection abuse include those with a ‎history of prolonged use of any opioid, including products containing meperidine, those with a history of drug or alcohol abuse, or those who use DEMEROL Injection in ‎combination with other abused drugs.

“Drug-seeking” behavior is very common in persons with substance use disorders. Drug-seeking tactics include emergency calls or visits near the end of office hours, refusal to undergo appropriate examination, testing, or referral, repeated “loss” of prescriptions, tampering with prescriptions, and reluctance to provide prior medical records or contact information for other treating healthcare provider(s). “Doctor shopping” (visiting multiple prescribers to obtain additional prescriptions) is common among people who abuse drugs and people with substance use disorder. Preoccupation with achieving adequate pain relief can be appropriate behavior in a patient with inadequate pain control.

DEMEROL Injection, like other opioids, can be diverted for nonmedical use into illicit channels of distribution. Careful record-keeping of prescribing information, including quantity, frequency, and renewal requests, as required by state and federal law, is strongly advised.

Proper assessment of the patient, proper prescribing practices, periodic reevaluation of therapy, and proper dispensing and storage are appropriate measures that help to limit abuse of opioid drugs.

Risks Specific to Abuse of DEMEROL Injection

Abuse of DEMEROL Injection poses a risk of overdose and death. The risk is increased with concurrent abuse of DEMEROL Injection with alcohol and/or other CNS depressants.

Parenteral drug abuse is commonly associated with transmission of infectious diseases such as hepatitis and HIV.

9.3 Dependence

Both tolerance and physical dependence can develop during use of opioid therapy.

Tolerance is a physiological state characterized by a reduced response to a drug after repeated administration (i.e., a higher dose of a drug is required to produce the same effect that was once obtained at a lower dose).

Physical dependence is a state that develops as a result of a physiological adaptation in response to repeated drug use, manifested by withdrawal signs and symptoms after abrupt discontinuation or a significant dose reduction of a drug.

Withdrawal may be precipitated through the administration of drugs with opioid antagonist activity (e.g., naloxone, nalmefene), mixed agonist/antagonist analgesics (e.g., pentazocine, butorphanol, nalbuphine), or partial agonists (e.g., buprenorphine). Physical dependence may not occur to a clinically significant degree until after several days to weeks of continued use.

DEMEROL Injection should not be rapidly reduced or abruptly discontinued in a physically-dependent patient [see Dosage and Administration (2.4)]. If DEMEROL Injection is rapidly reduced or abruptly discontinued in a physically-dependent patient, a withdrawal syndrome may occur, typically characterized by restlessness, lacrimation, rhinorrhea, perspiration, chills, myalgia, and mydriasis. Other signs and symptoms also may develop, including irritability, anxiety, backache, joint pain, weakness, abdominal cramps, insomnia, nausea, anorexia, vomiting, diarrhea, or increased blood pressure, respiratory rate, or heart rate.

Infants born to mothers physically-dependent on opioids will also be physically-dependent and may exhibit respiratory difficulties and withdrawal signs [see Use in Specific Populations (8.1)].

10 OVERDOSAGE

Clinical Presentation

Acute overdose with meperidine can be manifested by respiratory depression, somnolence progressing to stupor or coma, skeletal muscle flaccidity, cold and clammy skin, constricted pupils, and, in some cases, pulmonary edema, bradycardia, hypotension, hypoglycemia, partial or complete airway obstruction, atypical snoring, and death. Marked mydriasis rather than miosis may be seen with hypoxia in overdose situations [see Clinical Pharmacology (12.2)]. Toxic leukoencephalopathy has been reported after opioid overdose and can present hours, days, or weeks after apparent recovery from the initial intoxication. In severe overdose, particularly by the intravenous route, apnea, circulatory collapse, cardiac arrest, and death may occur.

Accumulation of normeperidine as in chronic use or possibly following introduction of a concomitant CYP3A4 inducer presents as excitatory syndrome including hallucinations, tremors, muscle twitches, dilated pupils, hyperactive reflexes, and convulsions.

Treatment of Overdose

In case of overdose, priorities are the reestablishment of a patent and protected airway and institution of assisted or controlled ventilation, if needed. Employ other supportive measures (including oxygen and vasopressors) in the management of circulatory shock and pulmonary edema as indicated. Cardiac arrest or arrhythmias will require advanced life-support measures.

For clinically significant respiratory or circulatory depression secondary to meperidine overdose, administer an opioid overdose reversal agent such as naloxone or nalmefene.

Because the duration of opioid reversal is expected to be less than the duration of action of meperidine in DEMEROL Injection, carefully monitor the patient until spontaneous respiration is reliably re-established. If the response to an opioid overdose reversal agent is suboptimal or only brief in nature, administer additional reversal agent as directed by the product's prescribing information.

In an individual physically dependent on opioids, administration of the recommended usual dosage of the opioid overdose reversal agent will precipitate an acute withdrawal syndrome. The severity of the withdrawal symptoms experienced will depend on the degree of physical dependence and the dose of the reversal agent administered. If a decision is made to treat serious respiratory depression in the physically-dependent patient, administration of the reversal agent should be begun with care and by titration with smaller than usual doses of the reversal agent.

11 DESCRIPTION

DEMEROL (meperidine hydrochloride injection) is an opioid agonist available as a sterile aqueous solution, for intramuscular, intravenous, or subcutaneous administration. It contains meperidine hydrochloride as the active pharmaceutical ingredient. Meperidine hydrochloride chemical name is 4‑Piperidinecarboxylic acid, 1‑methyl-4-phenyl-,ethyl ester, hydrochloride. The molecular weight is 283.79 g/mol. Its molecular formula is C15H21NO2·HCl, and it has the following chemical structure.

Meperidine hydrochloride is a white crystalline substance with a melting point of 186° C to 189° C, and it is readily soluble in water.

DEMEROL (meperidine hydrochloride injection) is available as:

Single-dose CarpujectTM cartridge with Luer Lock for the Carpuject Syringe System: 25 mg/mL, 50 mg/mL, 75 mg/mL, and 100 mg/mL. Each mL of Single-dose cartridge contains 25 mg, 50 mg, 75 mg or 100 mg of meperidine hydrochloride USP (equivalent to 21.79 mg, 43.58 mg, 65.36 mg or 87.15 mg of meperidine), respectively, and sodium hydroxide NF, and hydrochloric acid NF as pH adjusters, in water for injection. Only the 25 mg strength contains 3.8 mg of sodium chloride USP as isotonicity agent.

Multiple-dose vials: 1,500 mg/30 mL (50 mg/mL) strength. Each mL of vial contains 50 mg of meperidine hydrochloride USP (equivalent to 43.58 mg of meperidine), 1 mg of meta-cresol USP, as a preservative, and sodium hydroxide NF, and hydrochloric acid NF as pH adjusters, in water for injection.

Single-dose NexJect™ Prefilled Syringe with Luer Lock: 25 mg/mL and 50 mg/mL strengths. Each mL contains 25 mg or 50 mg of meperidine hydrochloride USP (equivalent to 21.79 mg or 43.58 mg of meperidine), respectively, and sodium hydroxide NF, and hydrochloric acid NF as pH adjusters, in water for injection. Only the 25 mg strength contains 3.8 mg of sodium chloride USP as isotonicity agent.

The pH of DEMEROL (meperidine hydrochloride injection) solutions is between 3.5 and 6.0.

DEMEROL (meperidine hydrochloride injection) 5 percent solution has a specific gravity of 1.0086 at 20°C, and the 10 percent solution has a specific gravity of 1.0165 at 20°C.

12 CLINICAL PHARMACOLOGY

12.1 Mechanism of Action

Meperidine hydrochloride is an opioid agonist with multiple actions qualitatively similar to those of morphine; the most prominent of these involve the central nervous system and organs composed of smooth muscle. The principal actions of therapeutic value are analgesia and sedation.

12.2 Pharmacodynamics

Effects on the Central Nervous System

Meperidine produces respiratory depression by direct action on brain stem respiratory centers. The respiratory depression involves a reduction in the responsiveness of the brain stem respiratory centers to both increases in carbon dioxide tension and electrical stimulation.

Meperidine causes miosis, even in total darkness. Pinpoint pupils are a sign of opioid overdose but are not pathognomonic (e.g., pontine lesions of hemorrhagic or ischemic origins may produce similar findings). Marked mydriasis rather than miosis may be seen due to hypoxia in overdose situations.

Effects on the Gastrointestinal Tract and Other Smooth Muscle

Meperidine causes a reduction in motility associated with an increase in smooth muscle tone in the antrum of the stomach duodenum. Digestion of food in the small intestine is delayed and propulsive contractions are decreased. Propulsive peristaltic waves in the colon are decreased, while tone may be increased to the point of spasm, resulting in constipation. Other opioid-induced effects may include a reduction in biliary and pancreatic secretions, spasm of sphincter of Oddi, transient elevations in serum amylase, and opioid-induced esophageal dysfunction (OIED).

Effects of the Cardiovascular System

Meperidine produces peripheral vasodilation which may result in orthostatic hypotension or syncope. Manifestations of histamine release and/or peripheral vasodilation may include pruritus, flushing, red eyes, and sweating and/or orthostatic hypotension.

Effects on the Endocrine System

Opioids inhibit the secretion of adrenocorticotropic hormone (ACTH), cortisol, and luteinizing hormones (LH) in humans [see Adverse Reactions (6)]. They also stimulate prolactin, growth hormone (GH) secretion, and pancreatic secretion of insulin and glucagon.

Use of opioids for an extended period of time may influence the hypothalamic-pituitary-gonadal axis, leading to androgen deficiency that may manifest as low libido, impotence, erectile dysfunction, amenorrhea, or infertility. The causal role of opioids in the clinical syndrome of hypogonadism is unknown because the various medical, physical, lifestyle, and psychological stressors that may influence gonadal hormone levels have not been adequately controlled for in studies conducted to date [see Adverse Reactions (6)].

Effects on the Immune System

Opioids have been shown to have a variety of effects on components of the immune system in in vitro and animal models. The clinical significance of these findings is unknown. Overall, the effects of opioids appear to be modestly immunosuppressive.

Concentration–Efficacy Relationships

The minimum effective analgesic concentration will vary widely among patients, especially among patients who have been previously treated with opioid agonists. The minimum effective analgesic concentration of meperidine for any individual patient may increase over time due to an increase in pain, the development of a new pain syndrome and/or the development of analgesic tolerance [see Dosage and Administration (2.1, 2.2)].

Meperidine, in 60 mg to 80 mg parenteral doses, is approximately equivalent in analgesic effect to 10 mg of morphine. The onset of action is slightly more rapid than with morphine, and the duration of action is slightly shorter. Meperidine is significantly less effective by the oral than by the parenteral route, but the exact ratio of oral to parenteral effectiveness is unknown.

Concentration–Adverse Reaction Relationships

There is a relationship between increasing meperidine plasma concentration and increasing frequency of dose-related opioid adverse reactions such as nausea, vomiting, CNS effects, and respiratory depression. In opioid-tolerant patients, the situation may be altered by the development of tolerance to opioid-related adverse reactions [see Dosage and Administration (2.1, 2.2)].

12.3 Pharmacokinetics

Elimination

The half-life of meperidine is 2 to 5 hours, and the half-life of normeperidine is 15 to 30 hours.

Metabolism

Meperidine is metabolized through biotransformation. In vitro data show meperidine is metabolized to normeperidine in liver mainly by CYP3A4 and CYP2B6.

Excretion

Meperidine and normeperidine are excreted by kidneys.

Specific Population

Hepatic Impairment

The elimination half-life is 3 to 8 hours in healthy volunteers and is 1.3 to 2 times greater in post‑operative or cirrhotic patients.

Age

In clinical studies reported in the literature, changes in several pharmacokinetic parameters with increasing age have been observed. The initial volume of distribution and steady-state volume of distribution may be higher in elderly patients than in younger patients. The free fraction of meperidine in plasma may be higher in patients over 45 years of age than in younger patients.

Drug Interactions Studies

Phenytoin: The hepatic metabolism of meperidine may be enhanced by phenytoin. Concomitant administration resulted in reduced half-life and bioavailability with increased clearance of meperidine in healthy subjects; however, blood concentrations of normeperidine were increased [see Drug Interactions (7)].

Ritonavir: Plasma concentrations of the active metabolite normeperidine may be increased by ritonavir [see Drug Interactions (7)].

Acyclovir: Plasma concentrations of meperidine and its metabolite, normeperidine, may be increased by acyclovir [see Drug Interactions (7)].

Cimetidine: Cimetidine reduced the clearance and volume of distribution of meperidine and also the formation of the metabolite, normeperidine, in healthy subjects [see Drug Interactions (7)].

13 NONCLINICAL TOXICOLOGY

13.1 Carcinogenesis, Mutagenesis, Impairment of Fertility

Carcinogenesis

Long-term studies in animals to evaluate the carcinogenic potential of meperidine have not been conducted.

Mutagenesis

Studies in animals to evaluate the mutagenic potential of meperidine have not been conducted.

Impairment of Fertility

Studies to determine the effect of meperidine on fertility have not been conducted.

16 HOW SUPPLIED/STORAGE AND HANDLING

For Parenteral Use

DEMEROL (meperidine hydrochloride injection) is clear and colorless.

DEMEROL (meperidine hydrochloride injection) is supplied as a sterile solution in a multiple-dose vial, single-dose Carpuject™ cartridges for use ONLY with the Carpuject™ Holders and NexJect™ prefilled syringes for subcutaneous, intramuscular, and intravenous administration, and available as follows:

Unit of Sale | Concentration (per total volume)
NDC 0409-1181-30 Carton of 1 30 mL fill in 30 mL Multiple-dose Vial | 1,500 mg/30 mL (50 mg/mL)
NDC 0409-1176-30 Carton of 10 1 mL fill in 2.5 mL Carpuject™ Single-dose cartridge with Luer Lock | 25 mg/mL
NDC 0409-1178-30 Carton of 10 1 mL fill in 2.5 mL Carpuject™ Single-dose cartridge with Luer Lock | 50 mg/mL
NDC 0409-1179-30 Carton of 10 1 mL fill in 2.5 mL Carpuject™ Single-dose cartridge with Luer Lock | 75 mg/mL
NDC 0409-1180-69 Carton of 10 1 mL fill in 2.5 mL Carpuject™ Single-dose cartridge with Luer Lock | 100 mg/mL
NDC 0409-1362-01 Clamshell of 10 1 mL fill in 1.5 mL NexJect™ Single-dose Prefilled Syringe with Luer Lock | 25 mg/mL
NDC 0409-1418-01 Clamshell of 10 1 mL fill in 1.5 mL NexJect™ Single-dose Prefilled Syringe with Luer Lock | 50 mg/mL

Carpuject™ Single-dose cartridges are packaged in a Slim-Pak tamper detection package.

Note that a needle is not included with Carpuject™ Single-dose cartridges and NexJect™ Single-dose Prefilled Syringes.

CarpujectTM and NexJectTM Single-dose products: Discard unused portion.

Multiple-dose vials: Discard unused portion after 28 days.

STORAGE AND HANDLING

Store at 20°C to 25°C (68°F to 77°F), excursions permitted between 15°C to 30°C (59°F to 86°F). [See USP Controlled Room Temperature.]

17 PATIENT COUNSELING INFORMATION

Addiction, Abuse, and Misuse

Inform patients that the use of DEMEROL Injection, even when taken as recommended, can result in addiction, abuse, and misuse, which can lead to overdose and death [see Warnings and Precautions (5.1)]. Instruct patients not to share DEMEROL Injection with others and to take steps to protect DEMEROL Injection from theft or misuse.

Life-Threatening Respiratory Depression

Inform patients of the risk of life-threatening respiratory depression, including information that the risk is greatest when DEMEROL Injection or when the dosage is increased, and that it can occur even at recommended dosages [see Warnings and Precautions (5.2)].

Hyperalgesia and Allodynia

Advise patients to inform their healthcare provider if they experience symptoms of hyperalgesia, including worsening pain, increased sensitivity to pain, or new pain [see Warnings and Precautions (5.7), Adverse Reactions (6)].

Serotonin Syndrome

Inform patients that opioids could cause a rare but potentially life-threatening condition called serotonin syndrome resulting from concomitant administration of serotonergic drugs. Warn patients of the symptoms of serotonin syndrome and to seek medical attention right away if symptoms develop after discharge from the hospital. Instruct patients to inform their healthcare provider if they are taking, or plan to take serotonergic medications [see Warnings and Precautions (5.8), Drug Interactions (7)].

Constipation

Advise patients of the potential for severe constipation, including management instructions and when to seek medical attention [see Adverse Reactions (6), Clinical Pharmacology (12.1)].

Distributed by Hospira, Inc., Lake Forest, IL 60045 USA

For Medical Information about DEMEROL Injection, please visit www.pfizermedinfo.com or call 1‑800‑438‑1985.

LAB-0846-13.0

INSTRUCTIONS FOR USE

Parenteral drug products should be inspected visually for particulate matter and discoloration prior to ‎administration, whenever solution and container permit. Do not use if color is darker than pale yellow, if it ‎is discolored in any other way, or if it contains a precipitate.

Instructions for use - Carpuject™ Single-dose Cartridge

Carpuject™ Single-dose cartridges with Luer Lock are packaged in a Slim-Pak™ tamper detection package. Note that a needle is not included.

Before use, read all instructions for using the Carpuject™ Syringe, which are contained in the product insert for‎ the reusable Carpuject™ Holder before use.

Carpuject™ Single-dose cartridges are to be used ONLY with Carpuject™ Holders.

NOTE: To prevent needlestick injuries, do not recap, purposely bend, or break by hand used ‎needles. Do not recap, purposely bend, or break by hand blunt Cannulas.

Instructions for use - NexJect™ Single-dose Prefilled Syringe

NOTE: To prevent needlestick injuries, do not recap, purposely bend, or break by hand used ‎needles. Do not recap, purposely bend, or break by ‎hand blunt Cannulas.

Distributed by Hospira, Inc., Lake Forest, IL 60045 USA

LAB-1387-2.0

Revised: 12/2023

PRINCIPAL DISPLAY PANEL - 25 mg/mL Cartridge Label

1 mL Single-dose Carpuject™
Sterile Cartridge Unit with Luer Lock

Rx only
NDC 0409-1176-03

Demerol™
meperidine HCl injection, USP
25 mg/mL
CII

Dist. by Hospira, Inc., Lake Forest, IL 60045 USA
Hospira

PAA198797

#####AA
DMMMYYYY

PRINCIPAL DISPLAY PANEL - 25 mg/mL Cartridge Carton

NDC 0409-1176-30
Contains 10 of NDC 0409-1176-03
Rx only

1 mL Single-dose

10 Carpuject™
Sterile Cartridge Units
with Luer Lock

Needle not included

SLIM-PAK™
Tamper Detection Package

Demerol™
meperidine
hydrochloride
injection, USP
25 mg/mL
CII

For Intramuscular, Subcutaneous, or
Intravenous Use

Carpuject Cartridges are to be used
ONLY with Carpuject Holders.

Dist. by Hospira, Inc.,
Lake Forest, IL60045 USA
Hospira

PRINCIPAL DISPLAY PANEL - 50 mg/mL Cartridge Label

1 mL Single-dose Carpuject™
Sterile Cartridge Unit with Luer Lock

Rx only
NDC 0409-1178-03

Demerol™
meperidine HCl injection, USP
50 mg/mL
CII

Dist. by Hospira, Inc., Lake Forest, IL 60045 USA
Hospira

PAA198798

#####AA
DMMMYYYY

PRINCIPAL DISPLAY PANEL - 50 mg/mL Cartridge Carton

NDC 0409-1178-30
Contains 10 of NDC 0409-1178-03
Rx only

1 mL Single-dose

10 Carpuject™
Sterile Cartridge Units
with Luer Lock

Needle not included

SLIM-PAK™
Tamper Detection Package

Demerol™
meperidine
hydrochloride
injection, USP
50 mg/mL
CII

For Intramuscular, Subcutaneous, or
Intravenous Use

Carpuject Cartridges are to be used
ONLY with Carpuject Holders.

Dist. by Hospira, Inc.
Lake Forest, IL 60045 USA
Hospira

PRINCIPAL DISPLAY PANEL - 75 mg/mL Cartridge Label

1 mL Single-dose Carpuject™
Sterile Cartridge Unit with Luer Lock

Rx only
NDC 0409-1179-03

Demerol™
meperidine HCl injection, USP
75 mg/mL
CII

Dist. by Hospira, Inc., Lake Forest, IL 60045 USA
Hospira

PAA198799

#####AA
DMMMYYYY

PRINCIPAL DISPLAY PANEL - 75 mg/mL Cartridge Carton

NDC 0409-1179-30
Contains 10 of NDC 0409-1179-03
Rx only

1 mL Single-dose

10 Carpuject™
Sterile Cartridge Units
with Luer Lock

Needle not included

SLIM-PAK™
Tamper Detection Package

Demerol™
meperidine
hydrochloride
injection, USP
75 mg/mL
CII

For Intramuscular, Subcutaneous, or
Intravenous Use

Carpuject Cartridges are to be used
ONLY with Carpuject Holders.

Dist. by Hospira, Inc.
Lake Forest, IL 60045 USA
Hospira

PRINCIPAL DISPLAY PANEL - 100 mg/mL Cartridge Label

1 mL Single-dose Carpuject™
Sterile Cartridge Unit with Luer Lock

Rx only
NDC 0409-1180-59

Demerol™
meperidine HCl injection, USP
100 mg/mL
CII

Dist. by Hospira, Inc., Lake Forest, IL 60045 USA
Hospira

PAA198800

#####AA
DMMMYYYY

PRINCIPAL DISPLAY PANEL - 100 mg/mL Cartridge Carton

NDC 0409-1180-69
Contains 10 of NDC 0409-1180-59
Rx only

1 mL Single-dose

10 Carpuject™
Sterile Cartridge Units
with Luer Lock

Needle not included

SLIM-PAK™
Tamper Detection Package

Demerol™
meperidine
hydrochloride
injection, USP
100 mg/mL
CII

For Intramuscular, Subcutaneous, or
Intravenous Use

Carpuject Cartridges are to be used
ONLY with Carpuject Holders.

Dist. by Hospira, Inc.,
Lake Forest, IL 60045 USA
Hospira

PRINCIPAL DISPLAY PANEL - 30 mL Vial Label

30 mL
Multiple-dose vial

NDC 0409-1181-30
Rx only

Sterile Aqueous Injection

Demerol™
meperidine hydrochloride injection, USP
1500 mg/30 mL (50 mg/mL)
CII

For Intramuscular, Subcutaneous, or Intravenous Use

Distributed by
Hospira, Inc., Lake Forest, IL 60045 USA
Hospira

PRINCIPAL DISPLAY PANEL - 30 mL Vial Carton

NDC 0409-1181-30
Rx only
NSN 6505-00-126-9360

30 mL Multiple-dose vial

Demerol™
meperidine
hydrochloride
injection, USP
1500 mg/30 mL
(50 mg/mL)
CII

For Intramuscular, Subcutaneous,
or Intravenous Use

Sterile Aqueous Injection

Hospira

PRINCIPAL DISPLAY PANEL - 25 mg/mL Syringe Chamber Label

Demerol™
meperidine HCl injection, USP
CII
25 mg/mL
PAA148095

PRINCIPAL DISPLAY PANEL - 25 mg/mL Syringe Luer Label

TWIST & PULL

Tamper Seal

NDC 0409-1362-11
CII

Demerol™
meperidine HCl injection, USP

25 mg/mL

Intramuscular,
Subcutaneous, or
Intravenous Use
Rx only

1 mL Single-dose syringe

PAA148096

LOT #####AA
EXP DMMMYYYY

PRINCIPAL DISPLAY PANEL - 25 mg/mL Syringe Cello Pack

NDC 0409-1362-01
Demerol™
CII
meperidine hydrochloride
injection, USP

25 mg / mL

For Intramuscular, Subcutaneous, or Intravenous Use

10 NexJect™ 1 mL Single-dose syringes with luer lock
Rx only
Needle not included

Store at 20°C to 25°C (68°F to 77°F); excursions permitted between
15°C to 30°C (59°F to 86°F). [See USP Controlled Room Temperature.]
Sterile Aqueous Injection

Each mL contains 25 mg meperidine hydrochloride (equivalent to 21.79 mg
meperidine), 3.8 mg sodium chloride for isotonicity, NaOH and HCl for pH
adjustment, in water for injection.

For usual pediatric dosage and route of administration, see package insert.
Demerol™ is a registered trademark of Sanofi Pharmaceuticals, Inc.

PAA189910
Distributed by Hospira, Inc.
Lake Forest, IL 60045 USA
Hospira

PRINCIPAL DISPLAY PANEL - 50 mg/mL Syringe Chamber Label

Demerol™
meperidine HCl injection, USP
CII
50 mg/mL
PAA148098

PRINCIPAL DISPLAY PANEL - 50 mg/mL Syringe Luer Label

TWIST & PULL

Tamper Seal

NDC 0409-1418-11
CII

Demerol™
meperidine HCl injection, USP

50 mg/mL

Intramuscular,
Subcutaneous, or
Intravenous Use
Rx only
1 mL Single-dose syringe

PAA148099

LOT #####AA
EXP DMMMYYYY

PRINCIPAL DISPLAY PANEL - 50 mg/mL Syringe Cello Pack

NDC 0409-1418-01
Demerol™
CII
meperidine hydrochloride
injection, USP

50 mg / mL

For Intramuscular, Subcutaneous, or Intravenous Use

10 NexJect™ 1 mL Single-dose syringes with luer lock
Rx only
Needle not included

Store at 20°C to 25°C (68°F to 77°F); excursions permitted between
15°C to 30°C (59°F to 86°F). [See USP Controlled Room Temperature.]
Sterile Aqueous Injection

Each mL contains 50 mg meperidine hydrochloride (equivalent to 43.58 mg
meperidine), NaOH and HCl for pH adjustment, in water for injection.
For usual dosage and route of administration, see package insert.
Demerol™ is a registered trademark of Sanofi Pharmaceuticals, Inc.

PAA189961
Distributed by Hospira, Inc.
Lake Forest, IL 60045 USA
Hospira